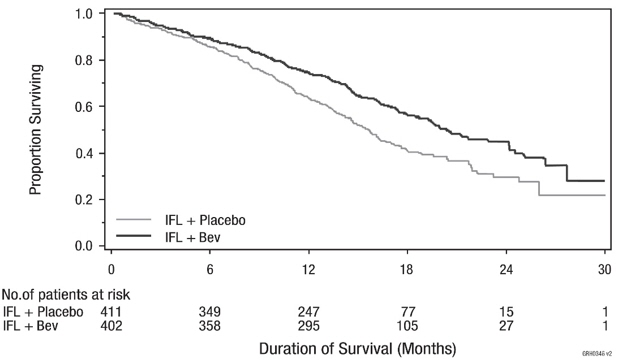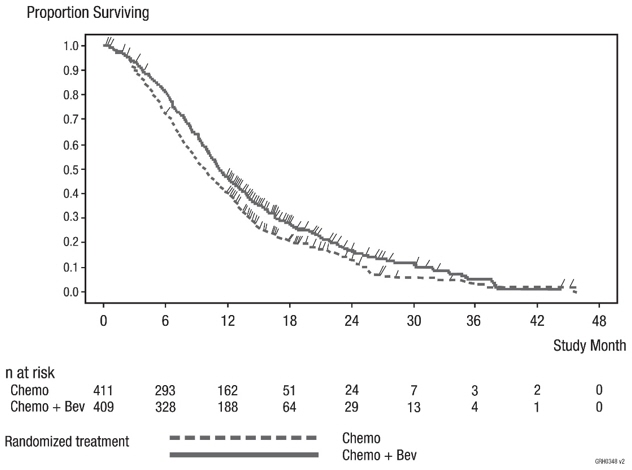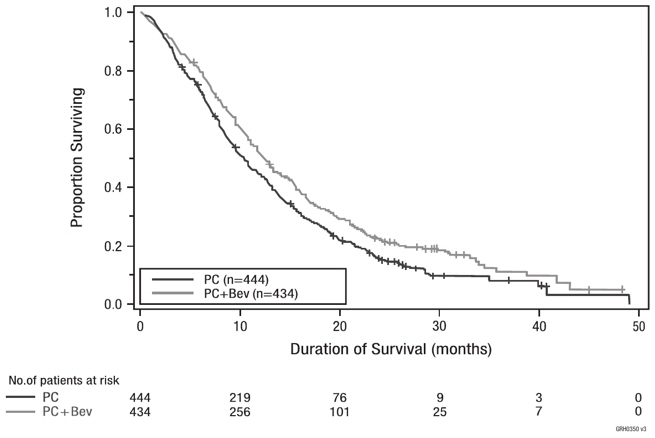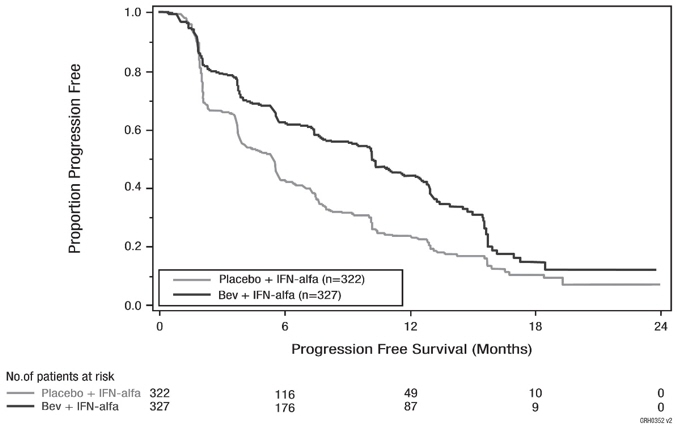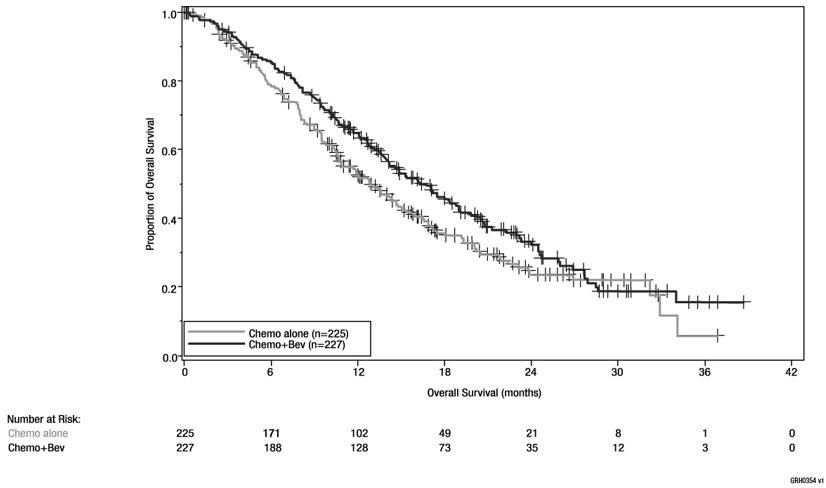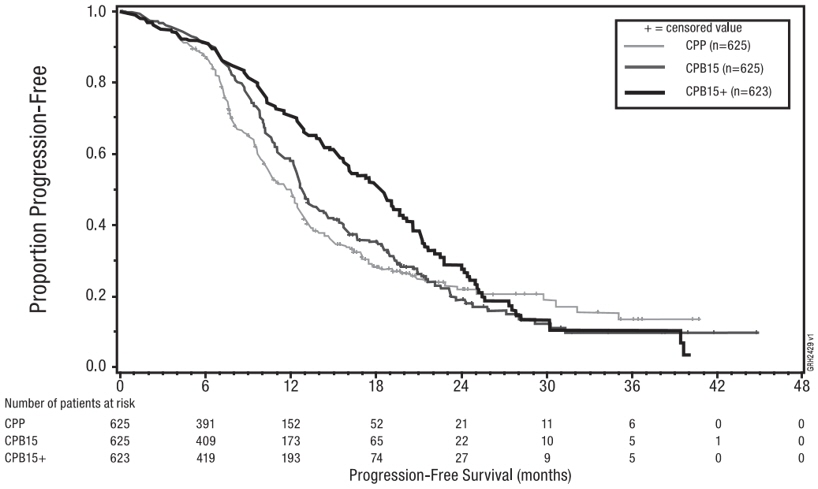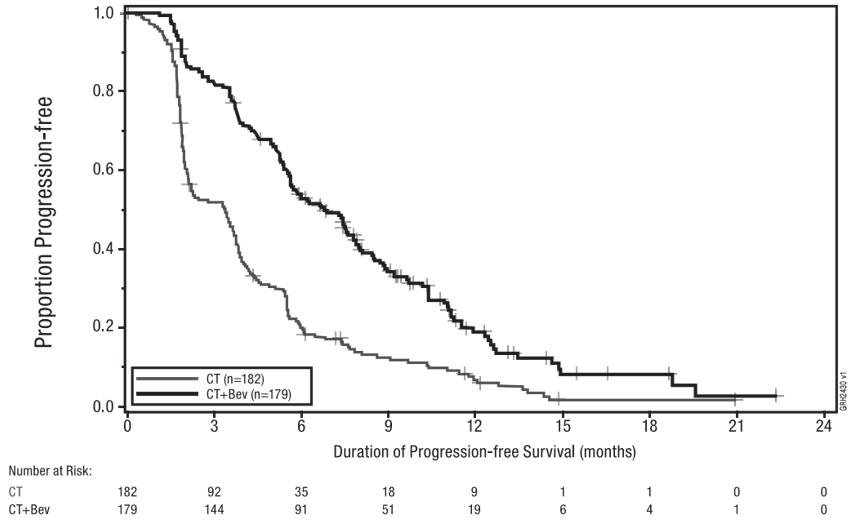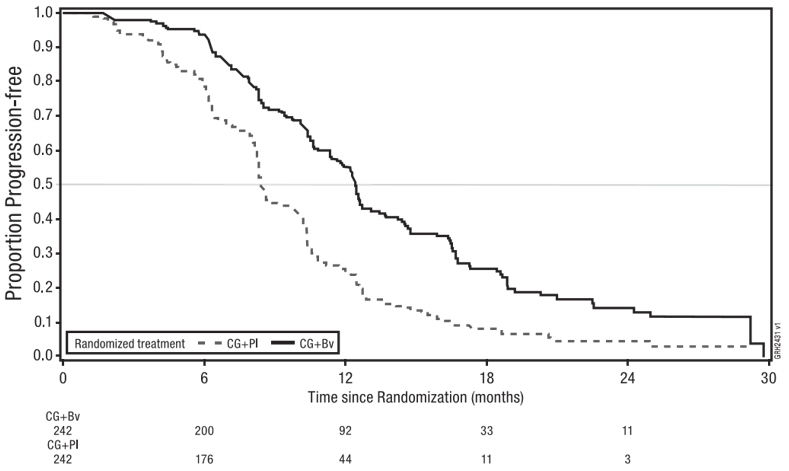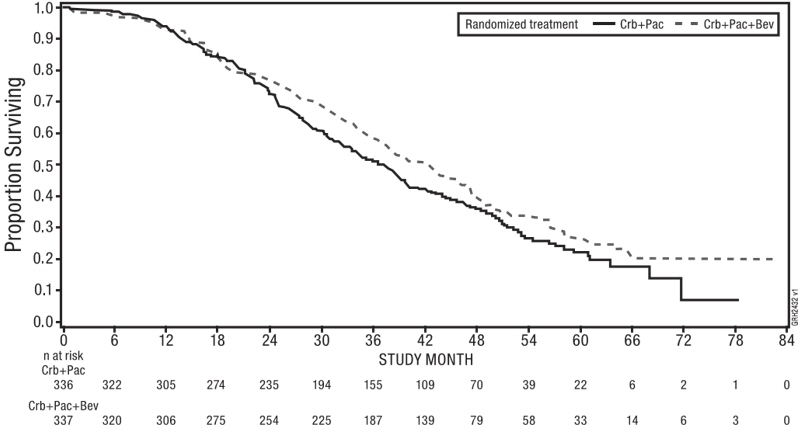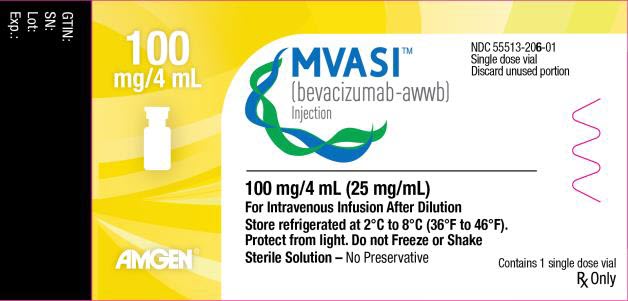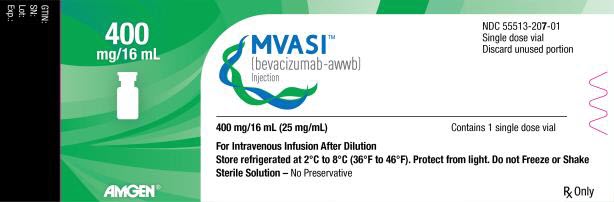 DRUG LABEL: MVASI
NDC: 55513-206 | Form: INJECTION, SOLUTION
Manufacturer: Amgen Inc
Category: prescription | Type: HUMAN PRESCRIPTION DRUG LABEL
Date: 20250623

ACTIVE INGREDIENTS: BEVACIZUMAB 100 mg/4 mL
INACTIVE INGREDIENTS: TREHALOSE DIHYDRATE 240 mg/4 mL; POLYSORBATE 20 1.6 mg/4 mL; SODIUM PHOSPHATE, DIBASIC, ANHYDROUS 4.8 mg/4 mL; SODIUM PHOSPHATE, MONOBASIC, MONOHYDRATE 23.2 mg/4 mL; WATER

HIGHLIGHTS OF PRESCRIBING INFORMATION

These highlights do not include all the information needed to use MVASI safely and effectively. See full prescribing information for MVASI.
MVASI® (bevacizumab-awwb) injection, for intravenous use
Initial U.S. Approval: 2017
MVASI (bevacizumab-awwb) is biosimilar [Biosimilar means that the biological product is approved based on data demonstrating that it is highly similar to an FDA-approved biological product, known as a reference product, and that there are no clinically meaningful differences between the biosimilar product and the reference product. Biosimilarity of MVASI has been demonstrated for the condition(s) of use (e.g., indication(s), dosing regimen(s)), strength(s), dosage form(s), and route(s) of administration described in its Full Prescribing Information.] to AVASTIN® (bevacizumab)

1 INDICATIONS AND USAGE

MVASI is a vascular endothelial growth factor inhibitor indicated for the treatment of:

- Metastatic colorectal cancer, in combination with intravenous fluorouracil-based chemotherapy for first- or second-line treatment. (1.1)
- Metastatic colorectal cancer, in combination with fluoropyrimidine-irinotecan- or fluoropyrimidine-oxaliplatin-based chemotherapy for second-line treatment in patients who have progressed on a first-line bevacizumab product-containing regimen. (1.1)
  Limitations of Use: MVASI is not indicated for adjuvant treatment of colon cancer. (1.1)
- Unresectable, locally advanced, recurrent or metastatic non-squamous non-small cell lung cancer, in combination with carboplatin and paclitaxel for first-line treatment. (1.2)
- Recurrent glioblastoma in adults. (1.3)
- Metastatic renal cell carcinoma in combination with interferon-alfa. (1.4)
- Persistent, recurrent, or metastatic cervical cancer, in combination with paclitaxel and cisplatin, or paclitaxel and topotecan. (1.5)
- Epithelial ovarian, fallopian tube, or primary peritoneal cancer:
  - in combination with carboplatin and paclitaxel, followed by MVASI as a single agent, for stage III or IV disease following initial surgical resection (1.6)
  - in combination with paclitaxel, pegylated liposomal doxorubicin, or topotecan for platinum-resistant recurrent disease who received no more than 2 prior chemotherapy regimens (1.6)
  - in combination with carboplatin and paclitaxel or carboplatin and gemcitabine, followed by MVASI as a single agent, for platinum-sensitive recurrent disease (1.6)

2 DOSAGE AND ADMINISTRATION

Withhold for at least 28 days prior to elective surgery. Do not administer MVASI for 28 days following major surgery and until adequate wound healing. (2.1)

Metastatic colorectal cancer (2.2)

- 5 mg/kg every 2 weeks with bolus-IFL
- 10 mg/kg every 2 weeks with FOLFOX4
- 5 mg/kg every 2 weeks or 7.5 mg/kg every 3 weeks with fluoropyrimidine-irinotecan or fluoropyrimidine-oxaliplatin based chemotherapy after progression on a first-line bevacizumab product-containing regimen

First-line non-squamous non-small cell lung cancer (2.3)

- 15 mg/kg every 3 weeks with carboplatin and paclitaxel

Recurrent glioblastoma (2.4)

- 10 mg/kg every 2 weeks

Metastatic renal cell carcinoma (2.5)

- 10 mg/kg every 2 weeks with interferon-alfa

Persistent, recurrent, or metastatic cervical cancer (2.6)

- 15 mg/kg every 3 weeks with paclitaxel and cisplatin or paclitaxel and topotecan

Stage III or IV epithelial ovarian, fallopian tube or primary peritoneal cancer following initial surgical resection (2.7)

- 15 mg/kg every 3 weeks with carboplatin and paclitaxel for up to 6 cycles, followed by 15 mg/kg every 3 weeks as a single agent, for a total of up to 22 cycles

Platinum-resistant recurrent epithelial ovarian, fallopian tube or primary peritoneal cancer (2.7)

- 10 mg/kg every 2 weeks with paclitaxel, pegylated liposomal doxorubicin, or topotecan given every week
- 15 mg/kg every 3 weeks with topotecan given every 3 weeks

Platinum-sensitive recurrent epithelial ovarian, fallopian tube, or primary peritoneal cancer (2.7)

- 15 mg/kg every 3 weeks with carboplatin and paclitaxel for 6-8 cycles, followed by 15 mg/kg every 3 weeks as a single agent
- 15 mg/kg every 3 weeks with carboplatin and gemcitabine for 6-10 cycles, followed by 15 mg/kg every 3 weeks as a single agent

Administer as an intravenous infusion after dilution. See full Prescribing Information for preparation and administration instructions and dosage modifications for adverse reactions (2.8, 2.9)

3 DOSAGE FORMS AND STRENGTHS

- Injection: 100 mg/4 mL (25 mg/mL) or 400 mg/16 mL (25 mg/mL) in a single-dose vial (3)

4 CONTRAINDICATIONS

None (4)

5 WARNINGS AND PRECAUTIONS

- Gastrointestinal Perforations and Fistula: Discontinue for gastrointestinal perforations, tracheoesophageal fistula, Grade 4 fistula, or fistula formation involving any organ. (5.1)
- Surgery and Wound Healing Complications: In patients who experience wound healing complications during MVASI treatment, withhold MVASI until adequate wound healing. Withhold for at least 28 days prior to elective surgery. Do not administer MVASI for at least 28 days following a major surgery, and until adequate wound healing. The safety of resumption of bevacizumab products after resolution of wound healing complication has not been established. Discontinue for wound healing complication of necrotizing fasciitis. (5.2)
- Hemorrhage: Severe or fatal hemorrhages have occurred. Do not administer for recent hemoptysis. Discontinue for Grade 3-4 hemorrhage. (5.3)
- Arterial Thromboembolic Events (ATE): Discontinue for severe ATE. (5.4)
- Venous Thromboembolic Events (VTE): Discontinue for Grade 4 VTE. (5.5)
- Hypertension: Monitor blood pressure and treat hypertension. Withhold if not medically controlled; resume once controlled. Discontinue for hypertensive crisis or hypertensive encephalopathy. (5.6)
- Posterior Reversible Encephalopathy Syndrome (PRES): Discontinue. (5.7)
- Renal Injury and Proteinuria: Monitor urine protein. Discontinue for nephrotic syndrome. Withhold until less than 2 grams of protein in urine. (5.8)
- Infusion-Related Reactions: Decrease rate for infusion-related reactions. Discontinue for severe infusion-related reactions and administer medical therapy. (5.9)
- Embryo-Fetal Toxicity: May cause fetal harm. Advise females of potential risk to fetus and need for use of effective contraception. (5.10, 8.1, 8.3)
- Ovarian Failure: Advise females of the potential risk. (5.11, 8.3)
- Congestive Heart Failure (CHF): Discontinue MVASI in patients who develop CHF. (5.12)

6 ADVERSE REACTIONS

Most common adverse reactions incidence (incidence > 10%) are epistaxis, headache, hypertension, rhinitis, proteinuria, taste alteration, dry skin, hemorrhage, lacrimation disorder, back pain and exfoliative dermatitis. (6.1)

To report SUSPECTED ADVERSE REACTIONS, contact Amgen Medical Information at 1-800-77-AMGEN (1-800-772-6436) or FDA at 1-800-FDA-1088 or www.fda.gov/medwatch.

8 USE IN SPECIFIC POPULATIONS

- Lactation: Advise not to breastfeed. (8.2)

FULL PRESCRIBING INFORMATION

1 INDICATIONS AND USAGE

1.1 Metastatic Colorectal Cancer

MVASI, in combination with intravenous fluorouracil-based chemotherapy, is indicated for the first- or second-line treatment of patients with metastatic colorectal cancer (mCRC).

MVASI, in combination with fluoropyrimidine-irinotecan- or fluoropyrimidine-oxaliplatin-based chemotherapy, is indicated for the second-line treatment of patients with mCRC who have progressed on a first-line bevacizumab product-containing regimen.

Limitations of Use: MVASI is not indicated for adjuvant treatment of colon cancer [see Clinical Studies (14.2)].

1.2 First-Line Non-Squamous Non-Small Cell Lung Cancer

MVASI, in combination with carboplatin and paclitaxel, is indicated for the first-line treatment of patients with unresectable, locally advanced, recurrent or metastatic non-squamous non-small cell lung cancer (NSCLC).

1.3 Recurrent Glioblastoma

MVASI is indicated for the treatment of recurrent glioblastoma (GBM) in adults.

1.4 Metastatic Renal Cell Carcinoma

MVASI, in combination with interferon-alfa, is indicated for the treatment of metastatic renal cell carcinoma (mRCC).

1.5 Persistent, Recurrent, or Metastatic Cervical Cancer

MVASI, in combination with paclitaxel and cisplatin or paclitaxel and topotecan, is indicated for the treatment of patients with persistent, recurrent, or metastatic cervical cancer.

1.6 Epithelial Ovarian, Fallopian Tube, or Primary Peritoneal Cancer

MVASI, in combination with carboplatin and paclitaxel, followed by MVASI as a single agent, is indicated for the treatment of patients with stage III or IV epithelial ovarian, fallopian tube, or primary peritoneal cancer following initial surgical resection.

MVASI, in combination with paclitaxel, pegylated liposomal doxorubicin, or topotecan, is indicated for the treatment of patients with platinum-resistant recurrent epithelial ovarian, fallopian tube or primary peritoneal cancer who received no more than 2 prior chemotherapy regimens.

MVASI, in combination with carboplatin and paclitaxel, or with carboplatin and gemcitabine, followed by MVASI as a single agent, is indicated for the treatment of patients with platinum-sensitive recurrent epithelial ovarian, fallopian tube, or primary peritoneal cancer.

2 DOSAGE AND ADMINISTRATION

2.1 Important Administration Information

Withhold for at least 28 days prior to elective surgery. Do not administer MVASI until at least 28 days following major surgery and until adequate wound healing.

2.2 Metastatic Colorectal Cancer

The recommended dosage when MVASI is administered in combination with intravenous fluorouracil-based chemotherapy is:

- 5 mg/kg intravenously every 2 weeks in combination with bolus-IFL.
- 10 mg/kg intravenously every 2 weeks in combination with FOLFOX4.
- 5 mg/kg intravenously every 2 weeks or 7.5 mg/kg intravenously every 3 weeks in combination with fluoropyrimidine-irinotecan- or fluoropyrimidine-oxaliplatin-based chemotherapy in patients who have progressed on a first-line bevacizumab product-containing regimen.

2.3 First-Line Non-Squamous Non-Small Cell Lung Cancer

The recommended dosage is 15 mg/kg intravenously every 3 weeks in combination with carboplatin and paclitaxel.

2.4 Recurrent Glioblastoma

The recommended dosage is 10 mg/kg intravenously every 2 weeks.

2.5 Metastatic Renal Cell Carcinoma

The recommended dosage is 10 mg/kg intravenously every 2 weeks in combination with interferon-alfa.

2.6 Persistent, Recurrent, or Metastatic Cervical Cancer

The recommended dosage is 15 mg/kg intravenously every 3 weeks in combination with paclitaxel and cisplatin, or in combination with paclitaxel and topotecan.

2.7 Epithelial Ovarian, Fallopian Tube, or Primary Peritoneal Cancer

Stage III or IV Disease Following Initial Surgical Resection

The recommended dosage is 15 mg/kg intravenously every 3 weeks in combination with carboplatin and paclitaxel for up to 6 cycles, followed by MVASI 15 mg/kg every 3 weeks as a single agent for a total of up to 22 cycles or until disease progression, whichever occurs earlier.

Recurrent Disease

Platinum Resistant

The recommended dosage is 10 mg/kg intravenously every 2 weeks in combination with paclitaxel, pegylated liposomal doxorubicin, or topotecan (every week).

The recommended dosage is 15 mg/kg intravenously every 3 weeks in combination with topotecan (every 3 weeks).

Platinum Sensitive

The recommended dosage is 15 mg/kg intravenously every 3 weeks, in combination with carboplatin and paclitaxel for 6 to 8 cycles, followed by MVASI 15 mg/kg every 3 weeks as a single agent until disease progression.

The recommended dosage is 15 mg/kg intravenously every 3 weeks, in combination with carboplatin and gemcitabine for 6 to 10 cycles, followed by MVASI 15 mg/kg every 3 weeks as a single agent until disease progression.

2.8 Dosage Modifications for Adverse Reactions

Table 1 describes dosage modifications for specific adverse reactions. No dose reductions for MVASI are recommended.

Table 1: Dosage Modifications for Adverse Reactions
Adverse Reaction | Severity | Dosage Modification
Gastrointestinal Perforations and Fistulae [see Warnings and Precautions (5.1)] | - Gastrointestinal perforation, any grade - Tracheoesophageal fistula, any grade - Fistula, Grade 4 - Fistula formation involving any internal organ | Discontinue MVASI
Wound Healing Complications [see Warnings and Precautions (5.2)] | - Any | Withhold MVASI until adequate wound healing. The safety of resumption of bevacizumab products after resolution of wound healing complications has not been established.
Wound Healing Complications [see Warnings and Precautions (5.2)] | - Necrotizing fasciitis | Discontinue MVASI
Hemorrhage [see Warnings and Precautions (5.3)] | - Grade 3 or 4 | Discontinue MVASI
Hemorrhage [see Warnings and Precautions (5.3)] | - Recent history of hemoptysis of 1/2 teaspoon (2.5 mL) or more | Withhold MVASI
Thromboembolic Events [see Warnings and Precautions (5.4, 5.5)] | - Arterial thromboembolism, severe | Discontinue MVASI
Thromboembolic Events [see Warnings and Precautions (5.4, 5.5)] | - Venous thromboembolism, Grade 4 | Discontinue MVASI
Hypertension [see Warnings and Precautions (5.6)] | - Hypertensive crisis - Hypertensive encephalopathy | Discontinue MVASI
Hypertension [see Warnings and Precautions (5.6)] | - Hypertension, severe | Withhold MVASI if not controlled with medical management; resume once controlled
Posterior Reversible Encephalopathy Syndrome (PRES) [see Warnings and Precautions (5.7)] | - Any | Discontinue MVASI
Renal Injury and Proteinuria [see Warnings and Precautions (5.8)] | - Nephrotic syndrome | Discontinue MVASI
Renal Injury and Proteinuria [see Warnings and Precautions (5.8)] | - Proteinuria greater than or equal to 2 grams per 24 hours in absence of nephrotic syndrome | Withhold MVASI until proteinuria less than 2 grams per 24 hours
Infusion-Related Reactions [see Warnings and Precautions (5.9)] | - Severe | Discontinue MVASI
Infusion-Related Reactions [see Warnings and Precautions (5.9)] | - Clinically significant | Interrupt infusion; resume at a decreased rate of infusion after symptoms resolve
Infusion-Related Reactions [see Warnings and Precautions (5.9)] | - Mild, clinically insignificant | Decrease infusion rate
Congestive Heart Failure [see Warnings and Precautions (5.12)] | Any | Discontinue MVASI

2.9 Preparation and Administration

Preparation

- Use appropriate aseptic technique.
- Use sterile needle and syringe to prepare MVASI.
- Visually inspect vial for particulate matter and discoloration prior to preparation for administration. Discard vial if solution is cloudy, discolored or contains particulate matter.
- Withdraw necessary amount of MVASI and dilute in a total volume of 100 mL of 0.9% Sodium Chloride Injection, USP. DO NOT ADMINISTER OR MIX WITH DEXTROSE SOLUTION.
- Discard any unused portion left in a vial, as the product contains no preservatives.
- Diluted MVASI solution may be stored at 2°C to 8°C (36°F to 46°F) for up to 8 hours, if not used immediately.
- No incompatibilities between MVASI and polyvinylchloride or polyolefin bags have been observed.

Administration

- Administer as an intravenous infusion.
- First infusion: Administer infusion over 90 minutes.
- Subsequent infusions: Administer second infusion over 60 minutes if first infusion is tolerated. Administer all subsequent infusions over 30 minutes if second infusion over 60 minutes is tolerated.

3 DOSAGE FORMS AND STRENGTHS

Injection: 100 mg/4 mL (25 mg/mL) or 400 mg/16 mL (25 mg/mL) clear to slightly opalescent, colorless to pale yellow solution in a single-dose vial.

4 CONTRAINDICATIONS

None.

5 WARNINGS AND PRECAUTIONS

5.1 Gastrointestinal Perforations and Fistulae

Serious, and sometimes fatal, gastrointestinal perforation occurred at a higher incidence in patients receiving bevacizumab products compared to patients receiving chemotherapy. The incidence ranged from 0.3% to 3% across clinical studies, with the highest incidence in patients with a history of prior pelvic radiation. Perforation can be complicated by intra-abdominal abscess, fistula formation, and the need for diverting ostomies. The majority of perforations occurred within 50 days of the first dose [see Adverse Reactions 6.1)].

Serious fistulae (including, tracheoesophageal, bronchopleural, biliary, vaginal, renal and bladder sites) occurred at a higher incidence in patients receiving bevacizumab products compared to patients receiving chemotherapy. The incidence ranged from < 1% to 1.8% across clinical studies, with the highest incidence in patients with cervical cancer. The majority of fistulae occurred within 6 months of the first dose. Patients who develop a gastrointestinal vaginal fistula may also have a bowel obstruction and require surgical intervention, as well as a diverting ostomy.

Avoid MVASI in patients with ovarian cancer who have evidence of recto-sigmoid involvement by pelvic examination or bowel involvement on CT scan or clinical symptoms of bowel obstruction. Discontinue in patients who develop gastrointestinal perforation, tracheoesophageal fistula or any Grade 4 fistula. Discontinue in patients with fistula formation involving any internal organ.

5.2 Surgery and Wound Healing Complications

In a controlled clinical study in which bevacizumab was not administered within 28 days of major surgical procedures, the incidence of wound healing complications, including serious and fatal complications, was 15% in patients with mCRC who underwent surgery while receiving bevacizumab and 4% in patients who did not receive bevacizumab. In a controlled clinical study in patients with relapsed or recurrent GBM, the incidence of wound healing events was 5% in patients who received bevacizumab and 0.7% in patients who did not receive bevacizumab [see Adverse Reactions (6.1)].

In patients who experience wound healing complications during MVASI treatment, withhold MVASI until adequate wound healing. Withhold for at least 28 days prior to elective surgery. Do not administer for at least 28 days following major surgery and until adequate wound healing. The safety of resumption of bevacizumab products after resolution of wound healing complications has not been established [see Dosage and Administration (2.7)].

Necrotizing fasciitis including fatal cases, has been reported in patients receiving bevacizumab, usually secondary to wound healing complications, gastrointestinal perforation or fistula formation. Discontinue MVASI in patients who develop necrotizing fasciitis.

5.3 Hemorrhage

Bevacizumab products can result in two distinct patterns of bleeding: minor hemorrhage, which is most commonly Grade 1 epistaxis, and serious hemorrhage, which in some cases has been fatal. Severe or fatal hemorrhage, including hemoptysis, gastrointestinal bleeding, hematemesis, CNS hemorrhage, epistaxis, and vaginal bleeding occurred up to 5-fold more frequently in patients receiving bevacizumab compared to patients receiving chemotherapy alone. Across clinical studies, the incidence of Grades 3-5 hemorrhagic events ranged from 0.4% to 7% in patients receiving bevacizumab [see Adverse Reactions (6.1)].

Serious or fatal pulmonary hemorrhage occurred in 31% of patients with squamous NSCLC and 4% of patients with non-squamous NSCLC receiving bevacizumab with chemotherapy compared to none of the patients receiving chemotherapy alone.

Do not administer MVASI to patients with recent history of hemoptysis of 1/2 teaspoon or more of red blood. Discontinue in patients who develop a Grade 3-4 hemorrhage.

5.4 Arterial Thromboembolic Events

Serious, sometimes fatal, arterial thromboembolic events (ATE) including cerebral infarction, transient ischemic attacks, myocardial infarction, and angina occurred at a higher incidence in patients receiving bevacizumab compared to patients receiving chemotherapy. Across clinical studies, the incidence of Grades 3-5 ATE was 5% in patients receiving bevacizumab with chemotherapy compared to ≤ 2% in patients receiving chemotherapy alone; the highest incidence occurred in patients with GBM. The risk of developing ATE was increased in patients with a history of arterial thromboembolism, diabetes, or >65 years [see Use in Specific Populations (8.5)].

Discontinue in patients who develop a severe ATE. The safety of reinitiating bevacizumab products after an ATE is resolved is not known.

5.5 Venous Thromboembolic Events

An increased risk of venous thromboembolic events (VTE) was observed across clinical studies [see Adverse Reactions (6.1)]. In Study GOG-0240, Grades 3-4 VTE occurred in 11% of patients receiving bevacizumab with chemotherapy compared with 5% of patients receiving chemotherapy alone. In EORTC 26101, the incidence of Grades 3-4 VTE was 5% in patients receiving bevacizumab with chemotherapy compared to 2% in patients receiving chemotherapy alone.

Discontinue MVASI in patients with a Grade 4 VTE, including pulmonary embolism.

5.6 Hypertension

Severe hypertension occurred at a higher incidence in patients receiving bevacizumab products as compared to patients receiving chemotherapy alone. Across clinical studies the incidence of Grades 3-4 hypertension ranged from 5% to 18%.

Monitor blood pressure every two to three weeks during treatment with MVASI. Treat with appropriate anti-hypertensive therapy and monitor blood pressure regularly. Continue to monitor blood pressure at regular intervals in patients with MVASI-induced or -exacerbated hypertension after discontinuing MVASI. Withhold MVASI in patients with severe hypertension that is not controlled with medical management; resume once controlled with medical management. Discontinue in patients who develop hypertensive crisis or hypertensive encephalopathy.

5.7 Posterior Reversible Encephalopathy Syndrome

Posterior reversible encephalopathy syndrome (PRES) was reported in < 0.5% of patients across clinical studies. The onset of symptoms occurred from 16 hours to 1 year after the first dose. PRES is a neurological disorder which can present with headache, seizure, lethargy, confusion, blindness and other visual and neurologic disturbances. Mild to severe hypertension may be present. Magnetic resonance imaging is necessary to confirm the diagnosis of PRES.

Discontinue MVASI in patients who develop PRES. Symptoms usually resolve or improve within days after discontinuing bevacizumab products, although some patients have experienced ongoing neurologic sequelae. The safety of reinitiating bevacizumab products in patients who developed PRES is not known.

5.8 Renal Injury and Proteinuria

The incidence and severity of proteinuria was higher in patients receiving bevacizumab as compared to patients receiving chemotherapy. Grade 3 (defined as urine dipstick 4+ or > 3.5 grams of protein per 24 hours) to Grade 4 (defined as nephrotic syndrome) ranged from 0.7% to 7% in clinical studies. The overall incidence of proteinuria (all grades) was only adequately assessed in Study BO17705, in which the incidence was 20%. Median onset of proteinuria was 5.6 months (15 days to 37 months) after initiating bevacizumab. Median time to resolution was 6.1 months (95% CI: 2.8, 11.3). Proteinuria did not resolve in 40% of patients after median follow-up of 11.2 months and required discontinuation of bevacizumab in 30% of the patients who developed proteinuria [see Adverse Reactions (6.1)].

In an exploratory, pooled analysis of patients from seven randomized clinical studies, 5% of patients receiving bevacizumab with chemotherapy experienced Grades 2-4 (defined as urine dipstick 2+ or greater or > 1 gram of protein per 24 hours or nephrotic syndrome) proteinuria. Grades 2-4 proteinuria resolved in 74% of patients. Bevacizumab was reinitiated in 42% of patients. Of the 113 patients who reinitiated bevacizumab, 48% experienced a second episode of Grades 2-4 proteinuria.

Nephrotic syndrome occurred in < 1% of patients receiving bevacizumab across clinical studies, in some instances with fatal outcome. In a published case series, kidney biopsy of 6 patients with proteinuria showed findings consistent with thrombotic microangiopathy. Results of a retrospective analysis of 5805 patients who received bevacizumab with chemotherapy and 3713 patients who received chemotherapy alone, showed higher rates of elevated serum creatinine levels (between 1.5 to 1.9 times baseline levels) in patients who received bevacizumab. Serum creatinine levels did not return to baseline in approximately one-third of patients who received bevacizumab.

Monitor proteinuria by dipstick urine analysis for the development or worsening of proteinuria with serial urinalyses during MVASI therapy. Patients with a 2+ or greater urine dipstick reading should undergo further assessment with a 24-hour urine collection. Withhold for proteinuria greater than or equal to 2 grams per 24 hours and resume when less than 2 grams per 24 hours. Discontinue in patients who develop nephrotic syndrome.

Data from a postmarketing safety study showed poor correlation between UPCR (Urine Protein/Creatinine Ratio) and 24-hour urine protein [Pearson Correlation 0.39 (95% CI: 0.17, 0.57)].

5.9 Infusion-Related Reactions

Infusion-related reactions reported across clinical studies and postmarketing experience include hypertension, hypertensive crises associated with neurologic signs and symptoms, wheezing, oxygen desaturation, Grade 3 hypersensitivity, anaphylactoid/anaphylactic reactions, chest pain, headaches, rigors, and diaphoresis. In clinical studies, infusion-related reactions with the first dose occurred in < 3% of patients and severe reactions occurred in 0.4% of patients.

Decrease the rate of infusion for mild, clinically insignificant infusion-related reactions. Interrupt the infusion in patients with clinically significant infusion-related reactions and consider resuming at a slower rate following resolution. Discontinue in patients who develop a severe infusion-related reaction and administer appropriate medical therapy (e.g., epinephrine, corticosteroids, intravenous antihistamines, bronchodilators and/or oxygen).

5.10 Embryo-Fetal Toxicity

Based on its mechanism of action and findings from animal studies, bevacizumab products may cause fetal harm when administered to pregnant women. Congenital malformations were observed with the administration of bevacizumab to pregnant rabbits during organogenesis every 3 days at a dose as low as a clinical dose of 10 mg/kg. Furthermore, animal models link angiogenesis and VEGF and VEGFR2 to critical aspects of female reproduction, embryo-fetal development, and postnatal development. Advise pregnant women of the potential risk to a fetus. Advise females of reproductive potential to use effective contraception during treatment with MVASI and for 6 months after the last dose [see Use in Specific Populations (8.1, 8.3)].

5.11 Ovarian Failure

The incidence of ovarian failure was 34% vs. 2% in premenopausal women receiving bevacizumab with chemotherapy as compared to those receiving chemotherapy alone for adjuvant treatment of a solid tumor. After discontinuing bevacizumab, recovery of ovarian function at all time points during the post-treatment period was demonstrated in 22% of women receiving bevacizumab. Recovery of ovarian function is defined as resumption of menses, a positive serum β-HCG pregnancy test, or an FSH level < 30 mIU/mL during the post-treatment period. Long-term effects of bevacizumab products on fertility are unknown. Inform females of reproductive potential of the risk of ovarian failure prior to initiating MVASI [see Adverse Reactions (6.1), Use in Specific Populations (8.3)].

5.12 Congestive Heart Failure

MVASI is not indicated for use with anthracycline-based chemotherapy. The incidence of Grade ≥ 3 left ventricular dysfunction was 1% in patients receiving bevacizumab compared to 0.6% of patients receiving chemotherapy alone. Among patients who received prior anthracycline treatment, the rate of congestive heart failure (CHF) was 4% for patients receiving bevacizumab with chemotherapy as compared to 0.6% for patients receiving chemotherapy alone.

In previously untreated patients with a hematological malignancy, the incidence of CHF and decline in left-ventricular ejection fraction (LVEF) were increased in patients receiving bevacizumab with anthracycline-based chemotherapy compared to patients receiving placebo with the same chemotherapy regimen. The proportion of patients with a decline in LVEF from baseline of ≥ 20% or a decline from baseline of 10% to < 50%, was 10% in patients receiving bevacizumab with chemotherapy compared to 5% in patients receiving chemotherapy alone. Time to onset of left-ventricular dysfunction or CHF was 1 to 6 months after the first dose in at least 85% of the patients and was resolved in 62% of the patients who developed CHF in the bevacizumab arm compared to 82% in the placebo arm. Discontinue MVASI in patients who develop CHF.

6 ADVERSE REACTIONS

The following clinically significant adverse reactions are described elsewhere in the labeling:

- Gastrointestinal Perforations and Fistulae [see Warnings and Precautions (5.1)].
- Surgery and Wound Healing Complications [see Warnings and Precautions (5.2)].
- Hemorrhage [see Warnings and Precautions (5.3)].
- Arterial Thromboembolic Events [see Warnings and Precautions (5.4)].
- Venous Thromboembolic Events [see Warnings and Precautions (5.5)].
- Hypertension [see Warnings and Precautions (5.6)].
- Posterior Reversible Encephalopathy Syndrome [see Warnings and Precautions (5.7)].
- Renal Injury and Proteinuria [see Warnings and Precautions (5.8)].
- Infusion-Related Reactions [see Warnings and Precautions (5.9)].
- Ovarian Failure [see Warnings and Precautions (5.11)].
- Congestive Heart Failure [see Warnings and Precautions (5.12)].

6.1 Clinical Trials Experience

Because clinical studies are conducted under widely varying conditions, adverse reaction rates observed in the clinical studies of a drug cannot be directly compared to rates in the clinical studies of another drug and may not reflect the rates observed in practice.

The safety data in Warnings and Precautions and described below reflect exposure to bevacizumab in 4463 patients including those with mCRC (AVF2107g, E3200), non-squamous NSCLC (E4599), GBM (EORTC 26101), mRCC (BO17705), cervical cancer (GOG-0240), epithelial ovarian, fallopian tube, or primary peritoneal cancer (MO22224, AVF4095, GOG-0213, and GOG-0218), or another cancer, at the recommended dose and schedule for a median of 6 to 23 doses. The most common adverse reactions observed in patients receiving bevacizumab as a single agent or in combination with other anti-cancer therapies at a rate > 10% were epistaxis, headache, hypertension, rhinitis, proteinuria, taste alteration, dry skin, hemorrhage, lacrimation disorder, back pain and exfoliative dermatitis.

Across clinical studies, bevacizumab was discontinued in 8% to 22% of patients because of adverse reactions [see Clinical Studies (14)].

Metastatic Colorectal Cancer

In Combination with bolus-IFL

The safety of bevacizumab was evaluated in 392 patients who received at least one dose of bevacizumab in a double-blind, active-controlled study (AVF2107g), which compared bevacizumab (5 mg/kg every 2 weeks) with bolus-IFL to placebo with bolus-IFL in patients with mCRC [see Clinical Studies (14.1)]. Patients were randomized (1:1:1) to placebo with bolus-IFL, bevacizumab with bolus-IFL, or bevacizumab with fluorouracil and leucovorin. The demographics of the safety population were similar to the demographics of the efficacy population. All Grades 3–4 adverse reactions and selected Grades 1–2 adverse reactions (i.e., hypertension, proteinuria, thromboembolic events) were collected in the entire study population. Adverse reactions are presented in Table 2.

Table 2: Grades 3-4 Adverse Reactions Occurring at Higher Incidence (≥ 2%) in Patients Receiving Bevacizumab vs. Placebo in Study AVF2107g
Adverse Reaction [NCI-CTC version 3.] | Bevacizumab with IFL (N = 392) | Placebo with IFL (N = 396)
Hematology
Leukopenia | 37% | 31%
Neutropenia | 21% | 14%
Gastrointestinal
Diarrhea | 34% | 25%
Abdominal pain | 8% | 5%
Constipation | 4% | 2%
Vascular
Hypertension | 12% | 2%
Deep vein thrombosis | 9% | 5%
Intra-abdominal Thrombosis | 3% | 1%
Syncope | 3% | 1%
General
Asthenia | 10% | 7%
Pain | 8% | 5%

In Combination with FOLFOX4

The safety of bevacizumab was evaluated in 521 patients in an open-label, active-controlled study (E3200) in patients who were previously treated with irinotecan and fluorouracil for initial therapy for mCRC. Patients were randomized (1:1:1) to FOLFOX4, bevacizumab (10 mg/kg every 2 weeks prior to FOLFOX4 on Day 1) with FOLFOX4, or bevacizumab alone (10 mg/kg every 2 weeks). Bevacizumab was continued until disease progression or unacceptable toxicity.

The demographics of the safety population were similar to the demographics of the efficacy population.

Selected Grades 3–5 non-hematologic and Grades 4–5 hematologic occurring at a higher incidence (≥ 2%) in patients receiving bevacizumab with FOLFOX4 compared to FOLFOX4 alone were fatigue (19% vs. 13%), diarrhea (18% vs. 13%), sensory neuropathy (17% vs. 9%), nausea (12% vs. 5%), vomiting (11% vs. 4%), dehydration (10% vs. 5%), hypertension (9% vs. 2%), abdominal pain (8% vs. 5%), hemorrhage (5% vs. 1%), other neurological (5% vs. 3%), ileus (4% vs. 1%) and headache (3% vs. 0%). These data are likely to under-estimate the true adverse reaction rates due to the reporting mechanisms.

First-Line Non-Squamous Non-Small Cell Lung Cancer

The safety of bevacizumab was evaluated as first-line treatment in 422 patients with unresectable NSCLC who received at least one dose of bevacizumab in an active-controlled, open-label, multicenter trial (E4599) [see Clinical Studies (14.3)]. Chemotherapy-naïve patients with locally advanced, metastatic or recurrent non–squamous NSCLC were randomized (1:1) to receive six 21-day cycles of paclitaxel and carboplatin with or without bevacizumab (15 mg/kg every 3 weeks). After completion or upon discontinuation of chemotherapy, patients randomized to receive bevacizumab continued to receive bevacizumab alone until disease progression or until unacceptable toxicity. The trial excluded patients with predominant squamous histology (mixed cell type tumors only), CNS metastasis, gross hemoptysis (1/2 teaspoon or more of red blood), unstable angina, or receiving therapeutic anticoagulation. The demographics of the safety population were similar to the demographics of the efficacy population.

Only Grades 3-5 non-hematologic and Grades 4-5 hematologic adverse reactions were collected. Grades 3-5 non-hematologic and Grades 4-5 hematologic adverse reactions occurring at a higher incidence (≥ 2%) in patients receiving bevacizumab with paclitaxel and carboplatin compared with patients receiving chemotherapy alone were neutropenia (27% vs. 17%), fatigue (16% vs. 13%), hypertension (8% vs. 0.7%), infection without neutropenia (7% vs. 3%), venous thromboembolism (5% vs. 3%), febrile neutropenia (5% vs. 2%), pneumonitis/pulmonary infiltrates (5% vs. 3%), infection with Grade 3 or 4 neutropenia (4% vs. 2%), hyponatremia (4% vs. 1%), headache (3% vs. 1%) and proteinuria (3% vs. 0%).

Recurrent Glioblastoma

The safety of bevacizumab was evaluated in a multicenter, randomized, open-label study (EORTC 26101) in patients with recurrent GBM following radiotherapy and temozolomide of whom 278 patients received at least one dose of bevacizumab and are considered safety evaluable [see Clinical Studies (14.4)]. Patients were randomized (2:1) to receive bevacizumab (10 mg/kg every 2 weeks) with lomustine or lomustine alone until disease progression or unacceptable toxicity. The demographics of the safety population were similar to the demographics of the efficacy population. In the bevacizumab with lomustine arm, 22% of patients discontinued treatment due to adverse reactions compared with 10% of patients in the lomustine arm. In patients receiving bevacizumab with lomustine, the adverse reaction profile was similar to that observed in other approved indications.

Metastatic Renal Cell Carcinoma

The safety of bevacizumab was evaluated in 337 patients who received at least one dose of bevacizumab in a multicenter, double-blind study (BO17705) in patients with mRCC. Patients who had undergone a nephrectomy were randomized (1:1) to receive either bevacizumab (10 mg/kg every 2 weeks) or placebo with interferon-alfa [see Clinical Studies (14.5)]. Patients were treated until disease progression or unacceptable toxicity. The demographics of the safety population were similar to the demographics of the efficacy population.

Grades 3-5 adverse reactions occurring at a higher incidence (> 2%) were fatigue (13% vs. 8%), asthenia (10% vs. 7%), proteinuria (7% vs. 0%), hypertension (6% vs. 1%; including hypertension and hypertensive crisis), and hemorrhage (3% vs. 0.3%; including epistaxis, small intestinal hemorrhage, aneurysm ruptured, gastric ulcer hemorrhage, gingival bleeding, hemoptysis, hemorrhage intracranial, large intestinal hemorrhage, respiratory tract hemorrhage, and traumatic hematoma). Adverse reactions are presented in Table 3.

Table 3: Grades 1-5 Adverse Reactions Occurring at Higher Incidence (≥ 5%) of Patients Receiving Bevacizumab vs. Placebo with Interferon-Alfa in Study BO17705
Adverse Reaction [NCI-CTC version 3.] | Bevacizumab with Interferon-Alfa (N = 337) | Placebo with Interferon-Alfa (N = 304)
Metabolism and nutrition
Decreased appetite | 36% | 31%
Weight loss | 20% | 15%
General
Fatigue | 33% | 27%
Vascular
Hypertension | 28% | 9%
Respiratory, thoracic and mediastinal
Epistaxis | 27% | 4%
Dysphonia | 5% | 0%
Nervous system
Headache | 24% | 16%
Gastrointestinal
Diarrhea | 21% | 16%
Renal and urinary
Proteinuria | 20% | 3%
Musculoskeletal and connective tissue
Myalgia | 19% | 14%
Back pain | 12% | 6%

The following adverse reactions were reported at a 5-fold greater incidence in patients receiving bevacizumab with interferon-alfa compared to patients receiving placebo with interferon-alfa and not represented in Table 3: gingival bleeding (13 patients vs. 1 patient); rhinitis (9 vs. 0); blurred vision (8 vs. 0); gingivitis (8 vs. 1); gastroesophageal reflux disease (8 vs. 1); tinnitus (7 vs. 1); tooth abscess (7 vs. 0); mouth ulceration (6 vs. 0); acne (5 vs. 0); deafness (5 vs. 0); gastritis (5 vs. 0); gingival pain (5 vs. 0) and pulmonary embolism (5 vs. 1).

Persistent, Recurrent, or Metastatic Cervical Cancer

The safety of bevacizumab was evaluated in 218 patients who received at least one dose of bevacizumab in a multicenter study (GOG-0240) in patients with persistent, recurrent, or metastatic cervical cancer [see Clinical Studies (14.6)]. Patients were randomized (1:1:1:1) to receive paclitaxel and cisplatin with or without bevacizumab (15 mg/kg every 3 weeks), or paclitaxel and topotecan with or without bevacizumab (15 mg/kg every 3 weeks). The demographics of the safety population were similar to the demographics of the efficacy population.

Grades 3–4 adverse reactions occurring at a higher incidence (≥ 2%) in 218 patients receiving bevacizumab with chemotherapy compared to 222 patients receiving chemotherapy alone were abdominal pain (12% vs. 10%), hypertension (11% vs. 0.5%), thrombosis (8% vs. 3%), diarrhea (6% vs. 3%), anal fistula (4% vs. 0%), proctalgia (3% vs. 0%), urinary tract infection (8% vs. 6%), cellulitis (3% vs. 0.5%), fatigue (14% vs. 10%), hypokalemia (7% vs. 4%), hyponatremia (4% vs. 1%), dehydration (4% vs. 0.5%), neutropenia (8% vs. 4%), lymphopenia (6% vs. 3%), back pain (6% vs. 3%), and pelvic pain (6% vs. 1%). Adverse reactions are presented in Table 4.

Table 4: Grades 1-4 Adverse Reactions Occurring at Higher Incidence (≥ 5%) in Patients Receiving Bevacizumab with Chemotherapy vs. Chemotherapy Alone in Study GOG-0240
Adverse Reaction [NCI-CTC version 3.] | Bevacizumab with Chemotherapy (N = 218) | Chemotherapy (N = 222)
General
Fatigue | 80% | 75%
Peripheral edema | 15% | 22%
Metabolism and nutrition
Decreased appetite | 34% | 26%
Hyperglycemia | 26% | 19%
Hypomagnesemia | 24% | 15%
Weight loss | 21% | 7%
Hyponatremia | 19% | 10%
Hypoalbuminemia | 16% | 11%
Vascular
Hypertension | 29% | 6%
Thrombosis | 10% | 3%
Infections
Urinary tract infection | 22% | 14%
Infection | 10% | 5%
Nervous system
Headache | 22% | 13%
Dysarthria | 8% | 1%
Psychiatric
Anxiety | 17% | 10%
Respiratory, thoracic and mediastinal
Epistaxis | 17% | 1%
Renal and urinary
Increased blood creatinine | 16% | 10%
Proteinuria | 10% | 3%
Gastrointestinal
Stomatitis | 15% | 10%
Proctalgia | 6% | 1%
Anal fistula | 6% | 0.0%
Reproductive system and breast
Pelvic pain | 14% | 8%
Hematology
Neutropenia | 12% | 6%
Lymphopenia | 12% | 5%

Epithelial Ovarian, Fallopian Tube, or Primary Peritoneal Cancer

Stage III or IV Following Initial Surgical Resection

The safety of bevacizumab was evaluated in GOG-0218, a multicenter, randomized, double-blind, placebo controlled, three arm study, which evaluated the addition of bevacizumab to carboplatin and paclitaxel for the treatment of patients with stage III or IV epithelial ovarian, fallopian tube, or primary peritoneal cancer following initial surgical resection [see Clinical Studies (14.7)]. Patients were randomized (1:1:1) to carboplatin and paclitaxel without bevacizumab (CPP), carboplatin and paclitaxel with bevacizumab for up to six cycles (CPB15), or carboplatin and paclitaxel with bevacizumab for six cycles followed by bevacizumab as a single agent for up to 16 additional doses (CPB15+). Bevacizumab was given at 15 mg/kg every three weeks. On this trial, 1215 patients received at least one dose of bevacizumab. The demographics of the safety population were similar to the demographics of the efficacy population.

Grades 3-4 adverse reactions occurring at a higher incidence (≥2%) in either of the bevacizumab arms versus the control arm were fatigue (CPB15+ - 9%, CPB15 - 6%, CPP - 6%), hypertension (CPB15+ - 10%, CPB15 - 6%, CPP - 2%), thrombocytopenia (CPB15+ - 21%, CPB15 - 20%, CPP - 15%) and leukopenia (CPB15+ - 51%, CPB15 - 53%, CPP - 50%). Adverse reactions are presented in Table 5.

Table 5: Grades 1-5 Adverse Reactions Occurring at Higher Incidence (≥ 5%) in Patients Receiving Bevacizumab with Chemotherapy vs. Chemotherapy Alone in GOG-0218
Adverse Reaction [NCI-CTC version 3,] | Bevacizumab with carboplatin and paclitaxel followed by bevacizumab alone [CPB15+,] (N=608) | Bevacizumab with carboplatin and paclitaxel [CPB15,] (N= 607) | Carboplatin and paclitaxel [CPP] (N= 602)
General
Fatigue | 80% | 72% | 73%
Gastrointestinal
Nausea | 58% | 53% | 51%
Diarrhea | 38% | 40% | 34%
Stomatitis | 25% | 19% | 14%
Musculoskeletal and connective tissue
Arthralgia | 41% | 33% | 35%
Pain in extremity | 25% | 19% | 17%
Muscular weakness | 15% | 13% | 9%
Nervous system
Headache | 34% | 26% | 21%
Dysarthria | 12% | 10% | 2%
Vascular
Hypertension | 32% | 24% | 14%
Respiratory, thoracic and mediastinal
Epistaxis | 31% | 30% | 9%
Dyspnea | 26% | 28% | 20%
Nasal mucosal disorder | 10% | 7% | 4%

Platinum-Resistant Recurrent Epithelial Ovarian, Fallopian Tube, or Primary Peritoneal Cancer

The safety of bevacizumab was evaluated in 179 patients who received at least one dose of bevacizumab in a multicenter, open-label study (MO22224) in which patients were randomized (1:1) to bevacizumab with chemotherapy or chemotherapy alone in patients with platinum resistant, recurrent epithelial ovarian, fallopian tube, or primary peritoneal cancer that recurred within < 6 months from the most recent platinum based therapy [see Clinical Studies (14.8)]. Patients were randomized to receive bevacizumab 10 mg/kg every 2 weeks or 15 mg/kg every 3 weeks. Patients had received no more than 2 prior chemotherapy regimens. The trial excluded patients with evidence of recto-sigmoid involvement by pelvic examination or bowel involvement on CT scan or clinical symptoms of bowel obstruction. Patients were treated until disease progression or unacceptable toxicity. Forty percent of patients on the chemotherapy alone arm received bevacizumab alone upon progression. The demographics of the safety population were similar to the demographics of the efficacy population.

Grades 3-4 adverse reactions occurring at a higher incidence (≥ 2%) in 179 patients receiving bevacizumab with chemotherapy compared to 181 patients receiving chemotherapy alone were hypertension (6.7% vs. 1.1%) and palmar-plantar erythrodysaesthesia syndrome (4.5% vs. 1.7%). Adverse reactions are presented in Table 6.

Table 6: Grades 2–4 Adverse Reactions Occurring at Higher Incidence (≥ 5%) in Patients Receiving Bevacizumab with Chemotherapy vs. Chemotherapy Alone in Study MO22224
Adverse Reaction [NCI-CTC version 3] | Bevacizumab with Chemotherapy (N=179) | Chemotherapy (N=181)
Hematology
Neutropenia | 31% | 25%
Vascular
Hypertension | 19% | 6%
Nervous system
Peripheral sensory neuropathy | 18% | 7%
General
Mucosal inflammation | 13% | 6%
Renal and urinary
Proteinuria | 12% | 0.6%
Skin and subcutaneous tissue
Palmar-plantar erythrodysaesthesia | 11% | 5%
Infections
Infection | 11% | 4%
Respiratory, thoracic and mediastinal
Epistaxis | 5% | 0%

Platinum-Sensitive Recurrent Epithelial Ovarian, Fallopian Tube, or Primary Peritoneal Cancer

Study AVF4095g

The safety of bevacizumab was evaluated in 247 patients who received at least one dose of bevacizumab in a double-blind study (AVF4095g) in patients with platinum sensitive recurrent epithelial ovarian, fallopian tube, or primary peritoneal cancer [see Clinical Studies (14.9)]. Patients were randomized (1:1) to receive bevacizumab (15 mg/kg) or placebo every 3 weeks with carboplatin and gemcitabine for 6 to 10 cycles followed by bevacizumab or placebo alone until disease progression or unacceptable toxicity. The demographics of the safety population were similar to the demographics of the efficacy population.

Grades 3-4 adverse reactions occurring at a higher incidence (≥ 2%) in patients receiving bevacizumab with chemotherapy compared to placebo with chemotherapy were: thrombocytopenia (40% vs. 34%), nausea (4% vs. 1.3%), fatigue (6% vs. 4%), headache (4% vs. 0.9%), proteinuria (10% vs. 0.4%), dyspnea (4% vs. 1.7%), epistaxis (5% vs. 0.4%), and hypertension (17% vs. 0.9%). Adverse reactions are presented in Table 7.

Table 7: Grades 1–5 Adverse Reactions Occurring at a Higher Incidence (≥ 5%) in Patients Receiving Bevacizumab with Chemotherapy vs. Placebo with Chemotherapy in Study AVF4095g
Adverse Reaction [NCI-CTC version 3] | Bevacizumab with Carboplatin and Gemcitabine (N=247) | Placebo with Carboplatin and Gemcitabine (N=233)
General
Fatigue | 82% | 75%
Mucosal inflammation | 15% | 10%
Gastrointestinal
Nausea | 72% | 66%
Diarrhea | 38% | 29%
Stomatitis | 15% | 7%
Hemorrhoids | 8% | 3%
Gingival bleeding | 7% | 0%
Hematology
Thrombocytopenia | 58% | 51%
Respiratory, thoracic and mediastinal
Epistaxis | 55% | 14%
Dyspnea | 30% | 24%
Cough | 26% | 18%
Oropharyngeal pain | 16% | 10%
Dysphonia | 13% | 3%
Rhinorrhea | 10% | 4%
Sinus congestion | 8% | 2%
Nervous system
Headache | 49% | 30%
Dizziness | 23% | 17%
Vascular
Hypertension | 42% | 9%
Musculoskeletal and connective tissue
Arthralgia | 28% | 19%
Back pain | 21% | 13%
Psychiatric
Insomnia | 21% | 15%
Renal and urinary
Proteinuria | 20% | 3%
Injury and procedural
Contusion | 17% | 9%
Infections
Sinusitis | 15% | 9%

Study GOG-0213

The safety of bevacizumab was evaluated in an open-label, controlled study (GOG-0213) in 325 patients with platinum-sensitive recurrent epithelial ovarian, fallopian tube, or primary peritoneal cancer, who have not received more than one previous regimen of chemotherapy [see Clinical Studies (14.9)]. Patients were randomized (1:1) to receive carboplatin and paclitaxel for 6 to 8 cycles or bevacizumab (15 mg/kg every 3 weeks) with carboplatin and paclitaxel for 6 to 8 cycles followed by bevacizumab as a single agent until disease progression or unacceptable toxicity. The demographics of the safety population were similar to the demographics of the efficacy population.

Grades 3-4 adverse reactions occurring at a higher incidence (≥ 2%) in patients receiving bevacizumab with chemotherapy compared to chemotherapy alone were: hypertension (11% vs. 0.6%), fatigue (8% vs. 3%), febrile neutropenia (6% vs. 3%), proteinuria (8% vs. 0%), abdominal pain (6% vs. 0.9%), hyponatremia (4% vs. 0.9%), headache (3% vs. 0.9%), and pain in extremity (3% vs. 0%).

Adverse reactions are presented in Table 8.

Table 8: Grades 1–5 Adverse Reactions Occurring at Higher Incidence (≥ 5%) in Patients Receiving Bevacizumab with Chemotherapy vs. Chemotherapy Alone in Study GOG-0213
Adverse Reaction [NCI-CTC version 3] | Bevacizumab with Carboplatin and Paclitaxel (N=325) | Carboplatin and Paclitaxel (N=332)
Musculoskeletal and connective tissue
Arthralgia | 45% | 30%
Myalgia | 29% | 18%
Pain in extremity | 25% | 14%
Back pain | 17% | 10%
Muscular weakness | 13% | 8%
Neck pain | 9% | 0%
Vascular
Hypertension | 42% | 3%
Gastrointestinal
Diarrhea | 39% | 32%
Abdominal pain | 33% | 28%
Vomiting | 33% | 25%
Stomatitis | 33% | 16%
Nervous system
Headache | 38% | 20%
Dysarthria | 14% | 2%
Dizziness | 13% | 8%
Metabolism and nutrition
Decreased appetite | 35% | 25%
Hyperglycemia | 31% | 24%
Hypomagnesemia | 27% | 17%
Hyponatremia | 17% | 6%
Weight loss | 15% | 4%
Hypocalcemia | 12% | 5%
Hypoalbuminemia | 11% | 6%
Hyperkalemia | 9% | 3%
Respiratory, thoracic and mediastinal
Epistaxis | 33% | 2%
Dyspnea | 30% | 25%
Cough | 30% | 17%
Rhinitis allergic | 17% | 4%
Nasal mucosal disorder | 14% | 3%
Skin and subcutaneous tissue
Exfoliative rash | 23% | 16%
Nail disorder | 10% | 2%
Dry skin | 7% | 2%
Renal and urinary
Proteinuria | 17% | 1%
Increased blood creatinine | 13% | 5%
Hepatic
Increased aspartate aminotransferase | 15% | 9%
General
Chest pain | 8% | 2%
Infections
Sinusitis | 7% | 2%

6.2 Immunogenicity

As with all therapeutic proteins, there is a potential for immunogenicity. The detection of antibody formation is highly dependent on the sensitivity and the specificity of the assay. Additionally, the observed incidence of antibody (including neutralizing antibody) positivity in an assay may be influenced by several factors, including assay methodology, sample handling, timing of sample collection, concomitant medications, and underlying disease. For these reasons, comparison of the incidence of antibodies in the studies described below with the incidence of antibodies in other studies or to other bevacizumab products may be misleading.

In clinical studies for adjuvant treatment of a solid tumor, 0.6% (14/2233) of patients tested positive for treatment-emergent anti-bevacizumab antibodies as detected by an electrochemiluminescent (ECL) based assay. Among these 14 patients, three tested positive for neutralizing antibodies against bevacizumab using an enzyme-linked immunosorbent assay (ELISA). The clinical significance of these anti-bevacizumab antibodies is not known.

6.3 Postmarketing Experience

The following adverse reactions have been identified during postapproval use of bevacizumab products. Because these reactions are reported voluntarily from a population of uncertain size, it is not always possible to reliably estimate their frequency or establish a causal relationship to drug exposure.

General: Polyserositis
Cardiovascular: Pulmonary hypertension, Mesenteric venous occlusion
Gastrointestinal: Gastrointestinal ulcer, Intestinal necrosis, Anastomotic ulceration
Hemic and lymphatic: Pancytopenia
Hepatobiliary disorders: Gallbladder perforation
Musculoskeletal and Connective Tissue Disorders: Osteonecrosis of the jaw
Renal: Renal thrombotic microangiopathy (manifested as severe proteinuria)
Respiratory: Nasal septum perforation
Vascular: Arterial (including aortic) aneurysms, dissections, and rupture

7 DRUG INTERACTIONS

Effects of MVASI on Other Drugs

No clinically meaningful effect on the pharmacokinetics of irinotecan or its active metabolite SN38, interferon-alfa, carboplatin or paclitaxel was observed when bevacizumab was administered in combination with these drugs; however, 3 of the 8 patients receiving bevacizumab with paclitaxel and carboplatin had lower paclitaxel exposure after four cycles of treatment (at Day 63) than those at Day 0, while patients receiving paclitaxel and carboplatin alone had a greater paclitaxel exposure at Day 63 than at Day 0.

8 USE IN SPECIFIC POPULATIONS

8.1 Pregnancy

Risk Summary

Based on findings from animal studies and their mechanism of action [see Clinical Pharmacology (12.1)], bevacizumab products may cause fetal harm in pregnant women. Limited postmarketing reports describe cases of fetal malformations with use of bevacizumab products in pregnancy; however, these reports are insufficient to determine drug associated risks. In animal reproduction studies, intravenous administration of bevacizumab to pregnant rabbits every 3 days during organogenesis at doses approximately 1 to 10 times the clinical dose of 10 mg/kg produced fetal resorptions, decreased maternal and fetal weight gain and multiple congenital malformations including corneal opacities and abnormal ossification of the skull and skeleton including limb and phalangeal defects (see Data). Furthermore, animal models link angiogenesis and VEGF and VEGFR2 to critical aspects of female reproduction, embryofetal development, and postnatal development. Advise pregnant women of the potential risk to a fetus.

In the U.S. general population, the estimated background risk of major birth defects and miscarriage in clinically recognized pregnancies is 2% to 4% and 15% to 20%, respectively.

Data

Animal Data

Pregnant rabbits dosed with 10 mg/kg to 100 mg/kg bevacizumab (approximately 1 to 10 times the clinical dose of 10 mg/kg) every three days during the period of organogenesis (gestation day 6-18) exhibited decreases in maternal and fetal body weights and increased number of fetal resorptions.

There were dose-related increases in the number of litters containing fetuses with any type of malformation (42% for the 0 mg/kg dose, 76% for the 30 mg/kg dose, and 95% for the 100 mg/kg dose) or fetal alterations (9% for the 0 mg/kg dose, 15% for the 30 mg/kg dose, and 61% for the 100 mg/kg dose). Skeletal deformities were observed at all dose levels, with some abnormalities including meningocele observed only at the 100 mg/kg dose level. Teratogenic effects included: reduced or irregular ossification in the skull, jaw, spine, ribs, tibia and bones of the paws; fontanel, rib and hindlimb deformities; corneal opacity; and absent hindlimb phalanges.

8.2 Lactation

Risk Summary

No data are available regarding the presence of bevacizumab products in human milk, the effects on the breast fed infant, or the effects on milk production. Human IgG is present in human milk, but published data suggest that breast milk antibodies do not enter the neonatal and infant circulation in substantial amounts. Because of the potential for serious adverse reactions in breastfed infants, advise women not to breastfeed during treatment with MVASI and for 6 months after the last dose.

8.3 Females and Males of Reproductive Potential

Contraception

Females

Bevacizumab products may cause fetal harm when administered to a pregnant woman [see Use in Specific Populations (8.1)]. Advise females of reproductive potential to use effective contraception during treatment with MVASI and for 6 months after the last dose.

Infertility

Females

Bevacizumab products increase the risk of ovarian failure and may impair fertility. Inform females of reproductive potential of the risk of ovarian failure prior to the first dose of MVASI. Long-term effects of bevacizumab products on fertility are not known.

In a clinical study of 179 premenopausal women randomized to receive chemotherapy with or without bevacizumab, the incidence of ovarian failure was higher in patients who received bevacizumab with chemotherapy (34%) compared to patients who received chemotherapy alone (2%). After discontinuing bevacizumab with chemotherapy, recovery of ovarian function occurred in 22% of these patients [see Warnings and Precautions (5.11), Adverse Reactions (6.1)].

8.4 Pediatric Use

The safety and effectiveness of bevacizumab products in pediatric patients have not been established. In published literature reports, cases of non-mandibular osteonecrosis have been observed in patients under the age of 18 years who received bevacizumab. Bevacizumab products are not approved for use in patients under the age of 18 years.

Antitumor activity was not observed among eight pediatric patients with relapsed GBM who received bevacizumab and irinotecan. Addition of bevacizumab to standard of care did not result in improved event-free survival in pediatric patients enrolled in two randomized clinical studies, one in high grade glioma (n = 121) and one in metastatic rhabdomyosarcoma or non-rhabdomyosarcoma soft tissue sarcoma (n = 154).

Based on the population pharmacokinetics analysis of data from 152 pediatric and young adult patients with cancer (7 months to 21 years of age), bevacizumab clearance normalized by body weight in pediatrics was comparable to that in adults.

Juvenile Animal Toxicity Data

Juvenile cynomolgus monkeys with open growth plates exhibited physeal dysplasia following 4 to 26 weeks exposure at 0.4 to 20 times the recommended human dose (based on mg/kg and exposure). The incidence and severity of physeal dysplasia were dose-related and were partially reversible upon cessation of treatment.

8.5 Geriatric Use

In an exploratory, pooled analysis of 1745 patients from five randomized, controlled studies, 35% of patients were ≥ 65 years old. The overall incidence of ATE was increased in all patients receiving bevacizumab with chemotherapy as compared to those receiving chemotherapy alone, regardless of age; however, the increase in the incidence of ATE was greater in patients ≥ 65 years (8% vs. 3%) as compared to patients < 65 years (2% vs. 1%) [see Warnings and Precautions (5.4)].

11 DESCRIPTION

Bevacizumab-awwb is a vascular endothelial growth factor inhibitor. Bevacizumab-awwb is a recombinant humanized monoclonal IgG1 antibody that contains human framework regions and murine complementarity-determining regions. Bevacizumab-awwb has an approximate molecular weight of 149 kDa. Bevacizumab-awwb is produced in a mammalian cell (Chinese Hamster Ovary) expression system.

MVASI (bevacizumab-awwb) injection is a sterile, preservative-free, clear to slightly opalescent, colorless to pale yellow solution in a single-dose vial for intravenous use. MVASI contains bevacizumab-awwb at a concentration of 25 mg/mL in either 100 mg/4 mL or 400 mg/16 mL, single-dose vials.

Each mL of solution contains 25 mg bevacizumab-awwb, α,α-trehalose dihydrate (60 mg), polysorbate 20 (0.4 mg), sodium phosphate dibasic, anhydrous (1.2 mg), sodium phosphate monobasic, monohydrate (5.8 mg), and Water for Injection, USP. The pH is 6.2.

12 CLINICAL PHARMACOLOGY

12.1 Mechanism of Action

Bevacizumab products bind VEGF and prevent the interaction of VEGF to its receptors (Flt-1 and KDR) on the surface of endothelial cells. The interaction of VEGF with its receptors leads to endothelial cell proliferation and new blood vessel formation in in vitro models of angiogenesis. Administration of bevacizumab to xenotransplant models of colon cancer in nude (athymic) mice caused reduction of microvascular growth and inhibition of metastatic disease progression.

12.3 Pharmacokinetics

The pharmacokinetic profile of bevacizumab was assessed using an assay that measures total serum bevacizumab concentrations (i.e., the assay did not distinguish between free bevacizumab and bevacizumab bound to VEGF ligand). Based on a population pharmacokinetic analysis of 491 patients who received 1 to 20 mg/kg of bevacizumab every week, every 2 weeks, or every 3 weeks, bevacizumab pharmacokinetics are linear and the predicted time to reach more than 90% of steady state concentration is 84 days. The accumulation ratio following a dose of 10 mg/kg of bevacizumab once every 2 weeks is 2.8.

Population simulations of bevacizumab exposures provide a median trough concentration of 80.3 mcg/mL on Day 84 (10th, 90th percentile: 45, 128) following a dose of 5 mg/kg once every two weeks.

Distribution

The mean (% coefficient of variation [CV%]) central volume of distribution is 2.9 (22%) L.

Elimination

The mean (CV%) clearance is 0.23 (33) L/day. The estimated half-life is 20 days (11 to 50 days).

Specific Populations

The clearance of bevacizumab varied by body weight, sex, and tumor burden. After correcting for body weight, males had a higher bevacizumab clearance (0.26 L/day vs. 0.21 L/day) and a larger central volume of distribution (3.2 L vs. 2.7 L) than females. Patients with higher tumor burden (at or above median value of tumor surface area) had a higher bevacizumab clearance (0.25 L/day vs. 0.20 L/day) than patients with tumor burdens below the median. In Study AVF2107g, there was no evidence of lesser efficacy (hazard ratio for overall survival) in males or patients with higher tumor burden treated with bevacizumab as compared to females and patients with low tumor burden.

13 NONCLINICAL TOXICOLOGY

13.1 Carcinogenesis, Mutagenesis, Impairment of Fertility

No studies have been conducted to assess potential of bevacizumab products for carcinogenicity or mutagenicity.

Bevacizumab products may impair fertility. Female cynomolgus monkeys treated with 0.4 to 20 times the recommended human dose of bevacizumab exhibited arrested follicular development or absent corpora lutea as well as dose-related decreases in ovarian and uterine weights, endometrial proliferation, and the number of menstrual cycles. Following a 4- or 12-week recovery period, there was a trend suggestive of reversibility. After the 12-week recovery period, follicular maturation arrest was no longer observed, but ovarian weights were still moderately decreased. Reduced endometrial proliferation was no longer observed at the 12-week recovery time point; however, decreased uterine weight, absent corpora lutea, and reduced number of menstrual cycles remained evident.

13.2 Animal Toxicology and/or Pharmacology

Rabbits dosed with bevacizumab exhibited reduced wound healing capacity. Using full-thickness skin incision and partial thickness circular dermal wound models, bevacizumab dosing resulted in reductions in wound tensile strength, decreased granulation and re-epithelialization, and delayed time to wound closure.

14 CLINICAL STUDIES

14.1 Metastatic Colorectal Cancer

Study AVF2107g

The safety and efficacy of bevacizumab was evaluated in a double-blind, active-controlled study [AVF2107g (NCT00109070)] in 923 patients with previously untreated mCRC who were randomized (1:1:1) to placebo with bolus-IFL (irinotecan 125 mg/m^2, fluorouracil 500 mg/m^2, and leucovorin 20 mg/m^2 given once weekly for 4 weeks every 6 weeks), bevacizumab (5 mg/kg every 2 weeks) with bolus-IFL, or bevacizumab (5 mg/kg every 2 weeks) with fluorouracil and leucovorin. Enrollment to the bevacizumab with fluorouracil and leucovorin arm was discontinued, after enrollment of 110 patients in accordance with the protocol-specified adaptive design. Bevacizumab was continued until disease progression or unacceptable toxicity or for a maximum of 96 weeks. The main outcome measure was overall survival (OS).

The median age was 60 years; 60% were male, 79% were White, 57% had an ECOG performance status of 0, 21% had a rectal primary and 28% received prior adjuvant chemotherapy. The dominant site of disease was extra-abdominal in 56% of patients and was the liver in 38% of patients.

The addition of bevacizumab improved survival across subgroups defined by age (< 65 years, ≥ 65 years) and sex. Results are presented in Table 9 and Figure 1.

Table 9: Efficacy Results in Study AVF2107g
Efficacy Parameter | Bevacizumab with bolus-IFL (N = 402) | Placebo with bolus-IFL (N = 411)
Overall Survival
Median, in months | 20.3 | 15.6
Hazard ratio (95% CI) | 0.66 (0.54, 0.81)
p-value [by stratified log-rank test.] | < 0.001
Progression-Free Survival
Median, in months | 10.6 | 6.2
Hazard ratio (95% CI) | 0.54 (0.45, 0.66)
p-value | < 0.001
Overall Response Rate
Rate (%) | 45% | 35%
p-value [by χ^2 test.] | < 0.01
Duration of Response
Median, in months | 10.4 | 7.1

Figure 1: Kaplan-Meier Curves for Duration of Survival in Metastatic Colorectal Cancer in Study AVF2107g

Among the 110 patients randomized to bevacizumab with fluorouracil and leucovorin, median OS was 18.3 months, median progression-free survival (PFS) was 8.8 months, overall response rate (ORR) was 39%, and median duration of response was 8.5 months.

Study E3200

The safety and efficacy of bevacizumab were evaluated in a randomized, open-label, active-controlled study [E3200 (NCT00025337)] in 829 patients who were previously treated with irinotecan and fluorouracil for initial therapy for metastatic disease or as adjuvant therapy. Patients were randomized (1:1:1) to FOLFOX4 (Day 1: oxaliplatin 85 mg/m^2 and leucovorin 200 mg/m^2 concurrently, then fluorouracil 400 mg/m^2 bolus followed by 600 mg/m^2 continuously; Day 2: leucovorin 200 mg/m^2, then fluorouracil 400 mg/m^2 bolus followed by 600 mg/m^2 continuously; every 2 weeks), bevacizumab (10 mg/kg every 2 weeks prior to FOLFOX4 on Day 1) with FOLFOX4, or bevacizumab alone (10 mg/kg every 2 weeks). Bevacizumab was continued until disease progression or unacceptable toxicity. The main outcome measure was OS.

The bevacizumab alone arm was closed to accrual after enrollment of 244 of the planned 290 patients following a planned interim analysis by the data monitoring committee based on evidence of decreased survival compared to FOLFOX4 alone.

The median age was 61 years; 60% were male, 87% were White, 49% had an ECOG performance status of 0, 26% received prior radiation therapy, and 80% received prior adjuvant chemotherapy, 99% received prior irinotecan, with or without fluorouracil for metastatic disease, and 1% received prior irinotecan and fluorouracil as adjuvant therapy.

The addition of bevacizumab to FOLFOX4 resulted in significantly longer survival as compared to FOLFOX4 alone; median OS was 13.0 months vs. 10.8 months [hazard ratio (HR) 0.75 (95% CI: 0.63, 0.89), p-value of 0.001 stratified log-rank test] with clinical benefit seen in subgroups defined by age (< 65 years, ≥ 65 years) and sex. PFS and ORR based on investigator assessment were higher in patients receiving bevacizumab with FOLFOX4.

Study TRC-0301

The activity of bevacizumab with fluorouracil (as bolus or infusion) and leucovorin was evaluated in a single arm study [TRC-0301 (NCT00066846)] enrolling 339 patients with mCRC with disease progression following both irinotecan- and oxaliplatin-based chemotherapy. Seventy-three percent of patients received concurrent bolus fluorouracil and leucovorin. One objective partial response was verified in the first 100 evaluable patients for an ORR of 1% (95% CI: 0%, 5.5%).

Study ML18147

The safety and efficacy of bevacizumab were evaluated in a prospective, randomized, open-label, multinational, controlled study [ML18147 (NCT00700102)] in 820 patients with histologically confirmed mCRC who had progressed on a first-line bevacizumab-containing regimen. Patients were excluded if they progressed within 3 months of initiating first-line chemotherapy and if they received bevacizumab for less than 3 consecutive months in the first-line setting. Patients were randomized (1:1) within 3 months after discontinuing bevacizumab as first-line treatment to receive fluoropyrimidine-irinotecan- or fluoropyrimidine-oxaliplatin-based chemotherapy with or without bevacizumab (5 mg/kg every 2 weeks or 7.5 mg/kg every 3 weeks). The choice of second-line treatment was contingent upon first-line chemotherapy. Second-line treatment was administered until progressive disease or unacceptable toxicity. The main outcome measure was OS. A secondary outcome measure was ORR.

The median age was 63 years (21 to 84 years); 64% were male, 52% had an ECOG performance status of 1, 44% had an ECOG performance status of 0, 58% received irinotecan-based therapy as first-line treatment, 55% progressed on first-line treatment within 9 months, and 77% received their last dose of bevacizumab as first-line treatment within 42 days of being randomized. Second-line chemotherapy regimens were generally balanced between each arm.

The addition of bevacizumab to fluoropyrimidine-based chemotherapy resulted in a statistically significant prolongation of OS and PFS. There was no significant difference in ORR. Results are presented in Table 10 and Figure 2.

Table 10: Efficacy Results in Study ML18147
Efficacy Parameter | Bevacizumab with Chemotherapy (N = 409) | Chemotherapy (N = 411)
Overall Survival [p = 0.0057 by unstratified log-rank test.]
Median, in months | 11.2 | 9.8
Hazard ratio (95% CI) | 0.81 (0.69, 0.94)
Progression-Free Survival [p-value < 0.0001 by unstratified log-rank test.]
Median, in months | 5.7 | 4.0
Hazard ratio (95% CI) | 0.68 (0.59, 0.78)

Figure 2: Kaplan-Meier Curves for Duration of Survival in Metastatic Colorectal Cancer in Study ML18147

14.2 Lack of Efficacy in Adjuvant Treatment of Colon Cancer

Lack of efficacy of bevacizumab as an adjunct to standard chemotherapy for the adjuvant treatment of colon cancer was determined in two randomized, open-label, multicenter clinical studies. The first study [BO17920 (NCT00112918)] was conducted in 3451 patients with high-risk stage II and III colon cancer, who had undergone surgery for colon cancer with curative intent. Patients were randomized to receive bevacizumab at a dose equivalent to 2.5 mg/kg/week on either a 2-weekly schedule with FOLFOX4 (N = 1155), or on a 3-weekly schedule with XELOX (N = 1145) or FOLFOX4 alone (N = 1151). The main outcome measure was disease free survival (DFS) in patients with stage III colon cancer.

The median age was 58 years; 54% were male, 84% were White and 29% were ≥ 65 years. Eighty-three percent had stage III disease.

The addition of bevacizumab to chemotherapy did not improve DFS. As compared to FOLFOX4 alone, the proportion of stage III patients with disease recurrence or with death due to disease progression were numerically higher for patients receiving bevacizumab with FOLFOX4 or with XELOX. The hazard ratios for DFS were 1.17 (95% CI: 0.98, 1.39) for bevacizumab with FOLFOX4 versus FOLFOX4 alone and 1.07 (95% CI: 0.90, 1.28) for bevacizumab with XELOX versus FOLFOX4 alone. The hazard ratios for OS were 1.31 (95% CI = 1.03, 1.67) and 1.27 (95% CI = 1, 1.62) for the comparison of bevacizumab with FOLFOX4 versus FOLFOX4 alone and bevacizumab with XELOX versus FOLFOX4 alone, respectively. Similar lack of efficacy for DFS was observed in the bevacizumab-containing arms compared to FOLFOX4 alone in the high-risk stage II cohort.

In a second study [NSABP-C-08 (NCT00096278)], patients with stage II and III colon cancer who had undergone surgery with curative intent, were randomized to receive either bevacizumab administered at a dose equivalent to 2.5 mg/kg/week with mFOLFOX6 (N = 1354) or mFOLFOX6 alone (N = 1356). The median age was 57 years, 50% were male and 87% White. Seventy-five percent had stage III disease. The main outcome was DFS among stage III patients. The HR for DFS was 0.92 (95% CI: 0.77, 1.10). OS was not significantly improved with the addition of bevacizumab to mFOLFOX6 [HR 0.96 (95% CI: 0.75, 1.22)].

14.3 First-Line Non-Squamous Non-Small Cell Lung Cancer

Study E4599

The safety and efficacy of bevacizumab as first-line treatment of patients with locally advanced, metastatic, or recurrent non-squamous NSCLC was studied in a single, large, randomized, active-controlled, open-label, multicenter study [E4599 (NCT00021060)]. A total of 878 chemotherapy-naïve patients with locally advanced, metastatic or recurrent non-squamous NSCLC were randomized (1:1) to receive six 21-day cycles of paclitaxel (200 mg/m^2) and carboplatin (AUC 6) with or without bevacizumab 15 mg/kg. After completing or discontinuing chemotherapy, patients randomized to receive bevacizumab continued to receive bevacizumab alone until disease progression or until unacceptable toxicity. The trial excluded patients with predominant squamous histology (mixed cell type tumors only), CNS metastasis, gross hemoptysis (1/2 teaspoon or more of red blood), unstable angina, or receiving therapeutic anticoagulation. The main outcome measure was duration of survival.

The median age was 63 years; 54% were male, 43% were ≥ 65 years, and 28% had ≥ 5% weight loss at study entry. Eleven percent had recurrent disease. Of the 89% with newly diagnosed NSCLC, 12% had Stage IIIB with malignant pleural effusion and 76% had Stage IV disease.

OS was statistically significantly longer for patients receiving bevacizumab with paclitaxel and carboplatin compared with those receiving chemotherapy alone. Median OS was 12.3 months vs. 10.3 months [HR 0.80 (95% CI: 0.68, 0.94), final p-value of 0.013, stratified log-rank test]. Based on investigator assessment which was not independently verified, patients were reported to have longer PFS with bevacizumab with paclitaxel and carboplatin compared to chemotherapy alone. Results are presented in Figure 3.

Figure 3: Kaplan-Meier Curves for Duration of Survival in First-Line Non-Squamous Non-Small Cell Lung Cancer in Study E4599

In an exploratory analysis across patient subgroups, the impact of bevacizumab on OS was less robust in the following subgroups: women [HR 0.99 (95% CI: 0.79, 1.25)], patients ≥ 65 years [HR 0.91 (95% CI: 0.72, 1.14)] and patients with ≥ 5% weight loss at study entry [HR 0.96 (95% CI: 0.73, 1.26)].

Study BO17704

The safety and efficacy of bevacizumab in patients with locally advanced, metastatic or recurrent non-squamous NSCLC, who had not received prior chemotherapy was studied in another randomized, double-blind, placebo-controlled study [BO17704 (NCT00806923)]. A total of 1043 patients were randomized (1:1:1) to receive cisplatin and gemcitabine with placebo, bevacizumab 7.5 mg/kg or bevacizumab 15 mg/kg. The main outcome measure was PFS. Secondary outcome measure was OS.

The median age was 58 years; 36% were female and 29% were ≥ 65 years. Eight percent had recurrent disease and 77% had Stage IV disease.

PFS was significantly higher in both bevacizumab-containing arms compared to the placebo arm [HR 0.75 (95% CI: 0.62, 0.91), p-value of 0.0026 for bevacizumab 7.5 mg/kg and HR 0.82 (95% CI: 0.68, 0.98), p-value of 0.0301 for bevacizumab 15 mg/kg]. The addition of bevacizumab to cisplatin and gemcitabine failed to demonstrate an improvement in the duration of OS [HR 0.93 (95% CI: 0.78, 1.11), p-value of 0.420 for bevacizumab 7.5 mg/kg and HR 1.03 (95% CI: 0.86, 1.23), p-value of 0.761 for bevacizumab 15 mg/kg].

14.4 Recurrent Glioblastoma

Study EORTC 26101

The safety and efficacy of bevacizumab were evaluated in a multicenter, randomized (2:1), open-label study in patients with recurrent GBM (EORTC 26101, NCT01290939). Patients with first progression following radiotherapy and temozolomide were randomized (2:1) to receive bevacizumab (10 mg/kg every 2 weeks) with lomustine (90 mg/m^2 every 6 weeks) or lomustine (110 mg/m^2 every 6 weeks) alone until disease progression or unacceptable toxicity. Randomization was stratified by World Health Organization performance status (0 vs. > 0), steroid use (yes vs. no), largest tumor diameter (≤ 40 vs. > 40 mm), and institution. The main outcome measure was OS. Secondary outcome measures were investigator-assessed PFS and ORR per the modified Response Assessment in Neuro-oncology (RANO) criteria, health related quality of life (HRQoL), cognitive function, and corticosteroid use.

A total of 432 patients were randomized to receive lomustine alone (N = 149) or bevacizumab with lomustine (N = 283). The median age was 57 years; 24.8% of patients were ≥ 65 years. The majority of patients with were male (61%); 66% had a WHO performance status score > 0; and in 56% the largest tumor diameter was ≤ 40 mm. Approximately 33% of patients randomized to receive lomustine received bevacizumab following documented progression.

No difference in OS (HR 0.91, p-value of 0.4578) was observed between arms; therefore, all secondary outcome measures are descriptive only. PFS was longer in the bevacizumab with lomustine arm [HR 0.52 (95% CI: 0.41, 0.64)] with a median PFS of 4.2 months in the bevacizumab with lomustine arm and 1.5 months in the lomustine arm. Among the 50% of patients receiving corticosteroids at the time of randomization, a higher percentage of patients in the bevacizumab with lomustine arm discontinued corticosteroids (23% vs. 12%).

Study AVF3708g and Study NCI 06-C-0064E

The efficacy and safety of bevacizumab 10 mg/kg every 2 weeks in patients with previously treated GBM were evaluated in one single arm single center study (NCI 06-C-0064E) and a randomized noncomparative multicenter study [AVF3708g (NCT00345163)]. Response rates in both studies were evaluated based on modified WHO criteria that considered corticosteroid use. In AVF3708g, the response rate was 25.9% (95% CI: 17%, 36.1%) with a median duration of response of 4.2 months (95% CI: 3, 5.7). In Study NCI 06-C-0064E, the response rate was 19.6% (95% CI: 10.9%, 31.3%) with a median duration of response of 3.9 months (95% CI: 2.4, 17.4).

14.5 Metastatic Renal Cell Carcinoma

Study BO17705

The safety and efficacy of bevacizumab were evaluated in patients with treatment-naïve mRCC in a multicenter, randomized, double-blind, international study [BO17705 (NCT00738530)] comparing interferon-alfa and bevacizumab versus interferon alfa and placebo. A total of 649 patients who had undergone a nephrectomy were randomized (1:1) to receive either bevacizumab (10 mg/kg every 2 weeks; N = 327) or placebo (every 2 weeks; N = 322) with interferon-alfa (9 MIU subcutaneously three times weekly, for a maximum of 52 weeks). Patients were treated until disease progression or unacceptable toxicity. The main outcome measure was investigator-assessed PFS. Secondary outcome measures were ORR and OS.

The median age was 60 years (18 to 82 years); 70% were male and 96% were White. The study population was characterized by Motzer scores as follows: 28% favorable (0), 56% intermediate (1-2), 8% poor (3-5), and 7% missing.

PFS was statistically significantly prolonged among patients receiving bevacizumab compared to placebo; median PFS was 10.2 months vs. 5.4 months [HR 0.60 (95% CI: 0.49, 0.72), p-value < 0.0001, stratified log-rank test]. Among the 595 patients with measurable disease, ORR was also significantly higher (30% vs. 12%, p-value < 0.0001, stratified CMH test). There was no improvement in OS based on the final analysis conducted after 444 deaths, with a median OS of 23 months in the patients receiving bevacizumab with interferon-alfa and 21 months in patients receiving interferon alone [HR 0.86, (95% CI: 0.72, 1.04)]. Results are presented in Figure 4.

Figure 4: Kaplan-Meier Curves for Progression-Free Survival in Metastatic Renal Cell Carcinoma in Study BO17705

14.6 Persistent, Recurrent, or Metastatic Cervical Cancer

Study GOG-0240

The safety and efficacy of bevacizumab were evaluated in patients with persistent, recurrent, or metastatic cervical cancer in a randomized, four-arm, multicenter study comparing bevacizumab with chemotherapy versus chemotherapy alone [GOG-0240 (NCT00803062)]. A total of 452 patients were randomized (1:1:1:1) to receive paclitaxel and cisplatin with or without bevacizumab, or paclitaxel and topotecan with or without bevacizumab.

The dosing regimens for bevacizumab, paclitaxel, cisplatin and topotecan were as follows:

- Day 1: Paclitaxel 135 mg/m^2 over 24 hours, Day 2: cisplatin 50 mg/m^2 with bevacizumab;
- Day 1: Paclitaxel 175 mg/m^2 over 3 hours, Day 2: cisplatin 50 mg/m^2 with bevacizumab;
- Day 1: Paclitaxel 175 mg/m^2 over 3 hours with cisplatin 50 mg/m^2 with bevacizumab;
- Day 1: Paclitaxel 175 mg/m^2 over 3 hours with bevacizumab, Days 1-3: topotecan IV 0.75 mg/m^2 over 30 minutes.

Patients were treated until disease progression or unacceptable adverse reactions. The main outcome measure was OS. Secondary outcome measures included ORR.

The median age was 48 years (20 to 85 years). Of the 452 patients randomized at baseline, 78% of patients were White, 80% had received prior radiation, 74% had received prior chemotherapy concurrent with radiation, and 32% had a platinum-free interval (PFI) of less than 6 months. Patients had a GOG performance status of 0 (58%) or 1 (42%). Demographic and disease characteristics were balanced across arms.

Results are presented in Figure 5 and Table 11.

Figure 5: Kaplan-Meier Curves for Overall Survival in Persistent, Recurrent, or Metastatic Cervical Cancer in Study GOG-0240

Table 11: Efficacy Results in Study GOG-0240
Efficacy Parameter | Bevacizumab with Chemotherapy (N = 227) | Chemotherapy (N = 225)
Overall Survival
Median, in months [Kaplan-Meier estimates.] | 16.8 | 12.9
Hazard ratio (95% CI) | 0.74 (0.58;0.94)
p-value [log-rank test (stratified).] | 0.0132

The ORR was higher in patients who received bevacizumab with chemotherapy [45% (95% CI: 39, 52)] compared to patients who received chemotherapy alone [34% (95% CI: 28, 40)].

Table 12: Efficacy Results in Study GOG-0240
Efficacy Parameter | Topotecan and Paclitaxel with or without Bevacizumab (N = 223) | Cisplatin and Paclitaxel with or without Bevacizumab (N = 229)
Overall Survival
Median, in months [Kaplan-Meier estimates.] | 13.3 | 15.5
Hazard ratio (95% CI)] | 1.15 (0.91, 1.46)
p-value | 0.23

The HR for OS with bevacizumab with cisplatin and paclitaxel as compared to cisplatin and paclitaxel alone was 0.72 (95% CI: 0.51, 1.02). The HR for OS with bevacizumab with topotecan and paclitaxel as compared to topotecan and paclitaxel alone was 0.76 (95% CI: 0.55, 1.06).

14.7 Stage III or IV Epithelial Ovarian, Fallopian Tube, or Primary Peritoneal Cancer Following Initial Surgical Resection

Study GOG-0218

The safety and efficacy of bevacizumab were evaluated in a multicenter, randomized, double-blind, placebo controlled, three arm study [Study GOG-0218 (NCT00262847)] evaluating the effect of adding bevacizumab to carboplatin and paclitaxel for the treatment of patients with stage III or IV epithelial ovarian, fallopian tube, or primary peritoneal cancer (N=1873) following initial surgical resection. Patients were randomized (1:1:1) to one of the following arms:

- CPP: carboplatin (AUC 6) and paclitaxel (175 mg/m^2) for six cycles, with concurrent placebo started at cycle 2, followed by placebo alone every three weeks for a total of up to 22 cycles of therapy (n=625) or
- CPB15: carboplatin (AUC 6) and paclitaxel (175 mg/m^2) for six cycles, with concurrent bevacizumab started at cycle 2, followed by placebo alone every three weeks for a total of up to 22 cycles of therapy (n=625) or
- CPB15+: carboplatin (AUC 6) and paclitaxel (175 mg/m^2) for six cycles, with concurrent bevacizumab started at cycle 2, followed by bevacizumab as a single agent every three weeks for a total of up to 22 cycles of therapy (n=623).

The main outcome measure was investigator-assessed PFS. OS was a secondary outcome measure.

The median age was 60 years (range 22-89 years) and 28% of patients were >65 years of age.

Overall, approximately 50% of patients had a GOG PS of 0 at baseline, and 43% a GOG PS score of 1. Patients had either epithelial ovarian cancer (83%), primary peritoneal cancer (15%), or fallopian tube cancer (2%). Serous adenocarcinoma was the most common histologic type (85% in CPP and CPB15 arms, 86% in CPB15+ arm). Overall, approximately 34% of patients had resected FIGO Stage III with residual disease < 1 cm, 40% had resected Stage III with residual disease >1 cm, and 26% had resected Stage IV disease.

The majority of patients in all three treatment arms received subsequent antineoplastic treatment, 78.1% in the CPP arm, 78.6% in the CPB15 arm, and 73.2% in the CPB15+ arm. A higher proportion of patients in the CPP arm (25.3%) and CPB15 arm (26.6%) received at least one anti-angiogenic (including bevacizumab) treatment after discontinuing from study compared with the CPB15+ arm (15.6%).

Study results are presented in Table 13 and Figure 6.

Table 13: Efficacy Results in Study GOG-0218
Efficacy Parameter | Bevacizumab with carboplatin and paclitaxel followed by bevacizumab alone (N=623) | Bevacizumab with carboplatin and paclitaxel (N=625) | Carboplatin and paclitaxel (N= 625)
Progression-Free Survival per Investigator
Median, in months | 18.2 | 12.8 | 12.0
Hazard ratio (95% CI) [Relative to the control arm; stratified hazard ratio] | 0.62 (0.52, 0.75) | 0.83 (0.70, 0.98)
p –value [Two-sided p-value based on re-randomization test] | < 0.0001 | NS
Overall Survival [Final overall survival analysis]
Median, in months | 43.8 | 38.8 | 40.6
Hazard ratio (95% CI) | 0.89 (0.76, 1.05) | 1.06 (0.90, 1.24)
NS = not significant

Figure 6: Kaplan-Meier Curves for Investigator-Assessed Progression-Free Survival in Stage III or IV Epithelial Ovarian, Fallopian Tube, or Primary Peritoneal Cancer Following Initial Surgical Resection in Study GOG-0218

14.8 Platinum-Resistant Recurrent Epithelial Ovarian, Fallopian Tube, or Primary Peritoneal Cancer

Study MO22224

The safety and efficacy of bevacizumab were evaluated in a multicenter, open-label, randomized study [MO22224 (NCT00976911)] comparing bevacizumab with chemotherapy versus chemotherapy alone in patients with platinum-resistant, recurrent epithelial ovarian, fallopian tube, or primary peritoneal cancer that recurred within <6 months from the most recent platinum-based therapy (N=361). Patients had received no more than 2 prior chemotherapy regimens. Patients received one of the following chemotherapy regimens at the discretion of the investigator: paclitaxel (80 mg/m^2 on days 1, 8, 15 and 22 every 4 weeks; pegylated liposomal doxorubicin 40 mg/m^2 on day 1 every 4 weeks; or topotecan 4 mg/m^2 on days 1, 8 and 15 every 4 weeks or 1.25 mg/m^2 on days 1-5 every 3 weeks). Patients were treated until disease progression, unacceptable toxicity, or withdrawal. Forty percent of patients on the chemotherapy alone arm received bevacizumab alone upon progression. The main outcome measure was investigator-assessed PFS. Secondary outcome measures were ORR and OS.

The median age was 61 years (25 to 84 years) and 37% of patients were ≥65 years. Seventy-nine percent had measurable disease at baseline, 87% had baseline CA-125 levels ≥2 times ULN and 31% had ascites at baseline. Seventy-three percent had a PFI of 3 months to 6 months and 27% had PFI of <3 months. ECOG performance status was 0 for 59%, 1 for 34% and 2 for 7% of the patients.

The addition of bevacizumab to chemotherapy demonstrated a statistically significant improvement in investigator-assessed PFS, which was supported by a retrospective independent review analysis. Results for the ITT population are presented in Table 14 and Figure 7. Results for the separate chemotherapy cohorts are presented in Table 15.

Table 14: Efficacy Results in Study MO22224
Efficacy Parameter | Bevacizumab with Chemotherapy (N=179) | Chemotherapy (N=182)
Progression-Free Survival per Investigator
Median (95% CI), in months | 6.8 (5.6, 7.8) | 3.4 (2.1, 3.8)
HR (95% CI) [per stratified Cox proportional hazards model] | 0.38 (0.30, 0.49)
p-value [per stratified log-rank test] | <0.0001
Overall Survival
Median (95% CI), in months | 16.6 (13.7, 19.0) | 13.3 (11.9, 16.4)
HR (95% CI) | 0.89 (0.69, 1.14)
Overall Response Rate
Number of Patients with Measurable Disease at Baseline | 142 | 144
Rate, % (95% CI) | 28% (21%, 36%) | 13% (7%, 18%)
Duration of Response
Median, in months | 9.4 | 5.4

Figure 7: Kaplan-Meier Curves for Investigator-Assessed Progression-Free Survival in Platinum-Resistant Recurrent Epithelial Ovarian, Fallopian Tube, or Primary Peritoneal Cancer in Study MO22224

Table 15: Efficacy Results in Study MO22224 by Chemotherapy
Efficacy Parameter | Paclitaxel |  | Topotecan |  | Pegylated Liposomal Doxorubicin
Efficacy Parameter | Bevacizumab with Chemotherapy (N=60) | Chemotherapy (N=55) | Bevacizumab with Chemotherapy (N=57) | Chemotherapy (N=63) | Bevacizumab with Chemotherapy (N=62) | Chemotherapy (N=64)
Progression-Free Survival per Investigator
Median, in months (95% CI) | 9.6 (7.8, 11.5) | 3.9 (3.5, 5.5) | 6.2 (5.3, 7.6) | 2.1 (1.9, 2.3) | 5.1 (3.9, 6.3) | 3.5 (1.9, 3.9)
Hazard ratio [per stratified Cox proportional hazards model] (95% CI) | 0.47 (0.31, 0.72) |  | 0.24 (0.15, 0.38) |  | 0.47 (0.32, 0.71)
Overall Survival
Median, in months (95% CI) | 22.4 (16.7, 26.7) | 13.2 (8.2, 19.7) | 13.8 (11.0, 18.3) | 13.3 (10.4, 18.3) | 13.7 (11.0, 18.3) | 14.1 (9.9, 17.8)
Hazard ratio (95% CI) | 0.64 (0.41, 1.01) |  | 1.12 (0.73, 1.73) |  | 0.94 (0.63, 1.42)
Overall Response Rate
Number of patients with measurable disease at baseline | 45 | 43 | 46 | 50 | 51 | 51
Rate, % (95% CI) | 53 (39, 68) | 30 (17, 44) | 17 (6, 28) | 2 (0, 6) | 16 (6, 26) | 8 (0, 15)
Duration of Response
Median, in months | 11.6 | 6.8 | 5.2 | NE | 8.0 | 4.6
NE=Not Estimable

14.9 Platinum-Sensitive Recurrent Epithelial Ovarian, Fallopian Tube, or Primary Peritoneal Cancer

Study AVF4095g

The safety and efficacy of bevacizumab were evaluated in a randomized, double-blind, placebo-controlled study [AVF4095g (NCT00434642)] studying bevacizumab with chemotherapy versus chemotherapy alone in the treatment of patients with platinum-sensitive recurrent epithelial ovarian, fallopian tube, or primary peritoneal cancer who have not received prior chemotherapy in the recurrent setting or prior bevacizumab treatment (N=484). Patients were randomized (1:1) to receive bevacizumab (15 mg/kg day 1) or placebo every 3 weeks with carboplatin (AUC 4, day 1) and gemcitabine (1000 mg/m^2 on days 1 and 8) for 6 to 10 cycles followed by bevacizumab or placebo alone until disease progression or unacceptable toxicity. The main outcome measures were investigator-assessed PFS. Secondary outcome measures were ORR and OS.

The median age was 61 years (28 to 87 years) and 37% of patients were ≥65 years. All patients had measurable disease at baseline, 74% had baseline CA-125 levels >ULN (35 U/mL). The PFI was 6 months to 12 months in 42 % of patients and >12 months in 58% of patients. The ECOG performance status was 0 or 1 for 99.8% of patients.

A statistically significant prolongation in PFS was demonstrated among patients receiving bevacizumab with chemotherapy compared to those receiving placebo with chemotherapy (Table 16 and Figure 8). Independent radiology review of PFS was consistent with investigator assessment [HR 0.45 (95% CI: 0.35, 0.58)]. OS was not significantly improved with the addition of bevacizumab to chemotherapy [HR 0.95 (95% CI: 0.77, 1.17)].

Table 16: Efficacy Results in Study AVF4095g
Efficacy Parameter | Bevacizumab with Gemcitabine and Carboplatin (N=242) | Placebo with Gemcitabine and Carboplatin (N=242)
Progression-Free Survival
Median, in months | 12.4 | 8.4
Hazard ratio (95% CI) | 0.46 (0.37, 0.58)
p-value | < 0.0001
Overall Response Rate
% patients with overall response | 78% | 57%
p-value | < 0.0001

Figure 8: Kaplan-Meier Curves for Progression-Free Survival in Platinum-Sensitive Recurrent Epithelial Ovarian, Fallopian Tube, or Primary Peritoneal Cancer in Study AVF4095g

Study GOG-0213

The safety and efficacy of bevacizumab were evaluated in a randomized, controlled, open-label study [Study GOG0213 (NCT00565851)] of bevacizumab with chemotherapy versus chemotherapy alone in the treatment of patients with platinum-sensitive recurrent epithelial ovarian, fallopian tube, or primary peritoneal cancer, who have not received more than one previous regimen of chemotherapy (N=673). Patients were randomized (1:1) to receive carboplatin (AUC 5) and paclitaxel (175 mg/m^2 IV over 3 hours) every 3 weeks for 6 to 8 cycles (N=336) or bevacizumab (15 mg/kg) every 3 weeks with carboplatin (AUC 5) and paclitaxel (175 mg/m^2 IV over 3 hours) for 6 to 8 cycles followed by bevacizumab (15 mg/kg every 3 weeks) as a single agent until disease progression or unacceptable toxicity. The main outcome measure was OS. Other outcome measures were investigator-assessed PFS, and ORR.

The median age was 60 years (23 to 85 years) and 33% of patients were ≥ 65 years. Eighty-three percent had measurable disease at baseline and 74% had abnormal CA-125 levels at baseline. Ten percent of patients had received prior bevacizumab. Twenty-six percent had a PFI of 6 months to 12 months and 74% had a PFI of >12 months. GOG performance status was 0 or 1 for 99% of patients.

Results are presented in Table 17 and Figure 9.

Table 17: Efficacy Results in Study GOG-0213
Efficacy Parameter | Bevacizumab with Carboplatin and Paclitaxel (N=337) | Carboplatin and Paclitaxel (N=336)
Overall Survival
Median, in months | 42.6 | 37.3
Hazard ratio (95% CI) (IVRS) [HR was estimated from Cox proportional hazards models stratified by the duration of treatment free-interval prior to enrolling onto this study per IVRS (interactive voice response system) and secondary surgical debulking status.] | 0.84 (0.69, 1.01)
Hazard ratio (95% CI) (eCRF) [HR was estimated from Cox proportional hazards models stratified by the duration of platinum free-interval prior to enrolling onto this study per eCRF (electronic case report form) and secondary surgical debulking status.] | 0.82 (0.68, 0.996)
Progression-Free Survival
Median, in months | 13.8 | 10.4
Hazard ratio (95% CI) (IVRS) | 0.61 (0.51, 0.72)
Overall Response Rate
Number of patients with measurable disease at baseline | 274 | 286
Rate, % | 213 (78%) | 159 (56%)

Figure 9: Kaplan Meier Curves for Overall Survival in Platinum-Sensitive Recurrent Epithelial Ovarian, Fallopian Tube, or Primary Peritoneal Cancer in Study GOG-0213

16 HOW SUPPLIED/STORAGE AND HANDLING

MVASI (bevacizumab-awwb) injection is a clear to slightly opalescent, colorless to pale yellow, sterile solution for intravenous infusion supplied as single-dose vials in the following strengths: 100 mg/4 mL (25 mg/mL) (NDC 55513-206-01, 55513-206-21) and 400 mg/16 mL (25 mg/mL) (NDC 55513-207-01, 55513-207-21). Each carton contains one vial.

STORAGE AND HANDLING

Store refrigerated at 2°C to 8°C (36°F to 46°F) in the original carton until time of use to protect from light. Do not freeze or shake the vial or carton.

17 PATIENT COUNSELING INFORMATION

Gastrointestinal Perforations and Fistulae

Bevacizumab products may increase the risk of developing gastrointestinal perforations and fistulae. Advise patients to immediately contact their health care provider for high fever, rigors, persistent or severe abdominal pain, severe constipation, or vomiting [see Warnings and Precautions (5.1)].

Surgery and Wound Healing Complications

Bevacizumab products can increase the risk of wound healing complications. Instruct patients not to undergo surgery without first discussing this potential risk with their health care provider [see Warnings and Precautions (5.2)].

Hemorrhage

Bevacizumab products can increase the risk of hemorrhage. Advise patients to immediately contact their health care provider for signs and symptoms of serious or unusual bleeding including coughing or spitting blood [see Warnings and Precautions (5.3)].

Arterial and Venous Thromboembolic Events

Bevacizumab products increase the risk of arterial and venous thromboembolic events. Advise patients to immediately contact their health care provider for signs and symptoms of arterial or venous thromboembolism [see Warnings and Precautions (5.4, 5.5)].

Hypertension

Bevacizumab products can increase blood pressure. Advise patients that they will undergo routine blood pressure monitoring and to contact their health care provider if they experience changes in blood pressure [see Warnings and Precautions (5.6)].

Posterior Reversible Leukoencephalopathy Syndrome

Posterior reversible encephalopathy syndrome (PRES) has been associated with bevacizumab products treatment. Advise patients to immediately contact their health care provider for new onset or worsening neurological function [see Warnings and Precautions (5.7)].

Renal Injury and Proteinuria

Bevacizumab products increase the risk of proteinuria and renal injury, including nephrotic syndrome. Advise patients that treatment with MVASI requires regular monitoring of renal function and to contact their health care provider for proteinuria or signs and symptoms of nephrotic syndrome [see Warnings and Precautions (5.8)].

Infusion-Related Reactions

Bevacizumab products can cause infusion-related reactions. Advise patients to contact their health care provider immediately for signs or symptoms of infusion-related reactions [see Warnings and Precautions (5.9)].

Congestive Heart Failure

Bevacizumab products can increase the risk of developing congestive heart failure. Advise patients to contact their health care provider immediately for signs and symptoms of CHF [see Warnings and Precautions (5.12)].

Embryo-Fetal Toxicity

Advise female patients that bevacizumab products may cause fetal harm and to inform their health care provider with a known or suspected pregnancy [see Warnings and Precautions (5.10), Use in Specific Populations (8.1)]. Advise females of reproductive potential to use effective contraception during treatment with MVASI and for 6 months after the last dose [see Use in Specific Populations (8.3)].

Ovarian Failure

Bevacizumab products may lead to ovarian failure. Advise patients of potential options for preservation of ova prior to starting treatment [see Warnings and Precautions (5.11)].

Lactation

Advise women not to breastfeed during treatment with MVASI and for 6 months after the last dose [see Use in Specific Populations (8.2)].

MVASI® (bevacizumab-awwb)

Manufactured by:
Amgen, Inc.
One Amgen Center Drive
Thousand Oaks, CA 91320-1799
US License No. 1080

Marketed by Amgen Inc.

AMGEN and MVASI® (bevacizumab-awwb) are trademarks owned or licensed by Amgen Inc., its subsidiaries, or affiliates.

AVASTIN® (bevacizumab) is a registered trademark owned or licensed by Genentech Inc., its subsidiaries, or affiliates.

© 2017-2021, 2023, 2025 Amgen Inc. All rights reserved.

1xxxxxx- v6

PACKAGE LABEL

PRINCIPAL DISPLAY PANEL

100 mg/4 mL

MVASI™

(bevacizumab-awwb)

Injection

NDC 55513-206-01

Single dose vial

Discard unused portion

100 mg/4 mL (25 mg/mL)

Contains 1 single dose vial

For Intravenous Infusion After Dilution

Store refrigerated at 2°C to 8°C (36°F to 46°F).

Protect from light. Do not Freeze or Shake

Sterile Solution – No Preservative

Rx Only

AMGEN®

PACKAGE LABEL

PRINCIPAL DISPLAY PANEL

400 mg/16 mL

MVASI™

(bevacizumab-awwb)

Injection

NDC 55513-207-01

Single dose vial

Discard unused portion

400 mg/16 mL (25 mg/mL)

Contains 1 single dose vial

For Intravenous Infusion After Dilution

Store refrigerated at 2°C to 8°C (36°F to 46°F). Protect from light. Do not Freeze or Shake

Sterile Solution – No Preservative

Rx Only

AMGEN®